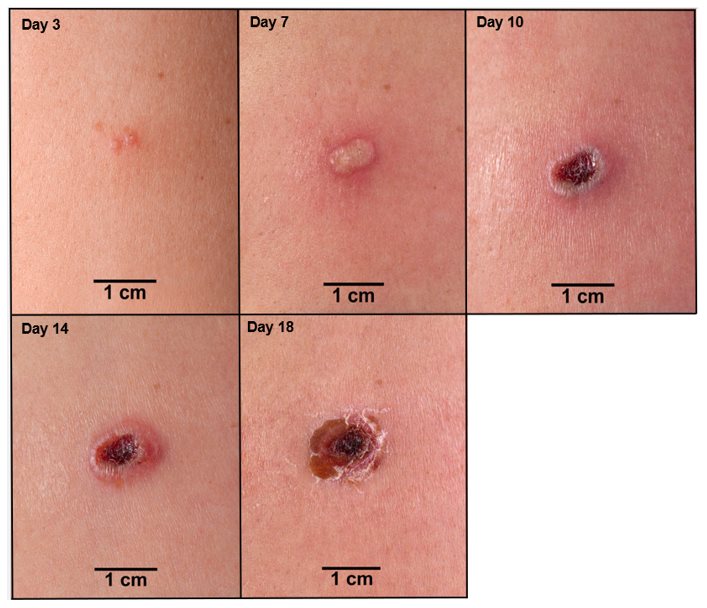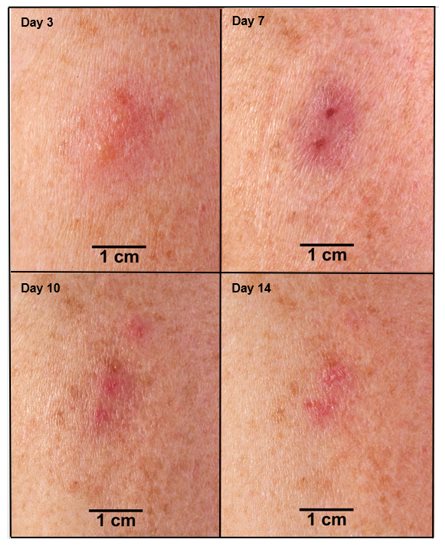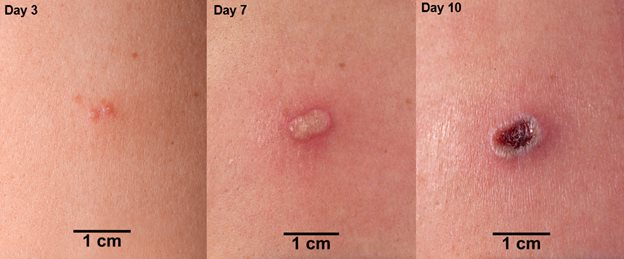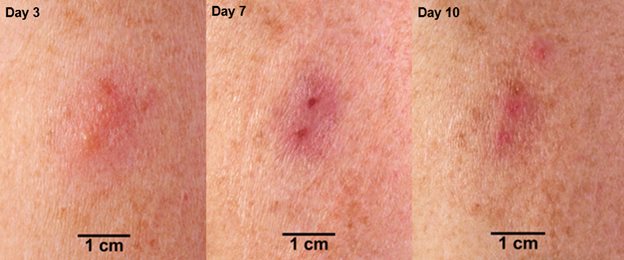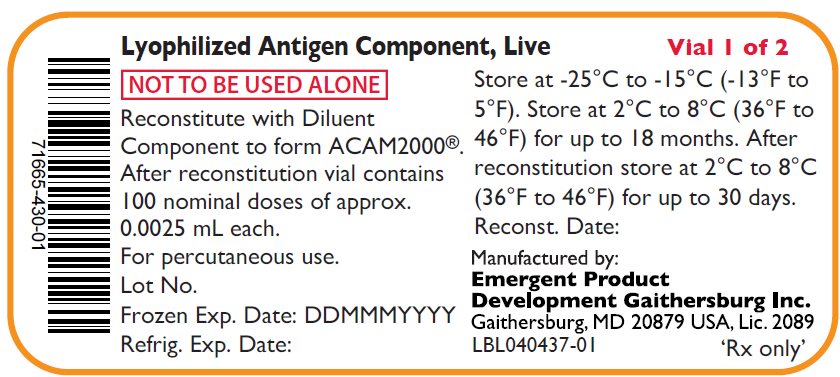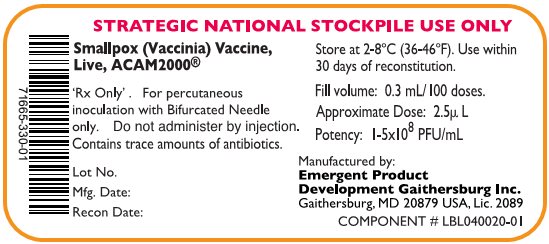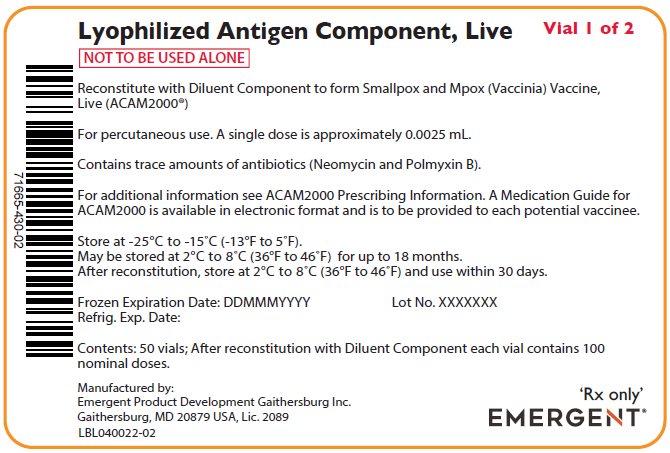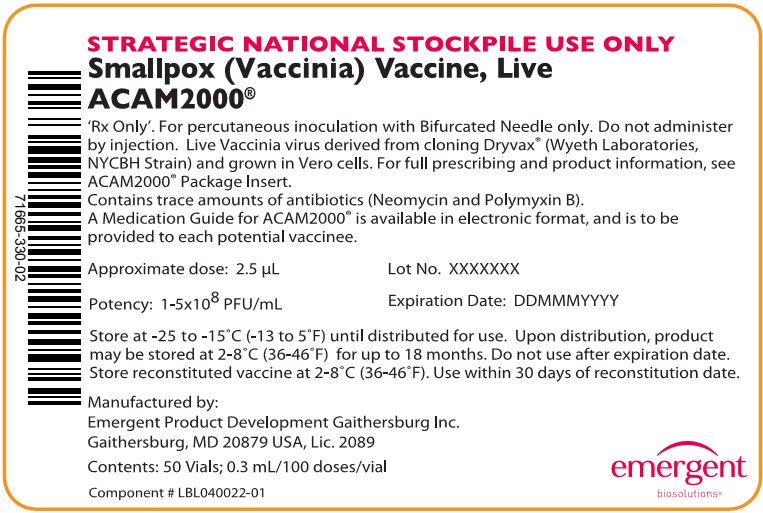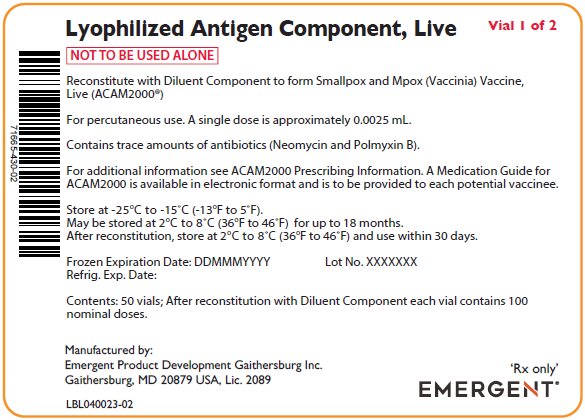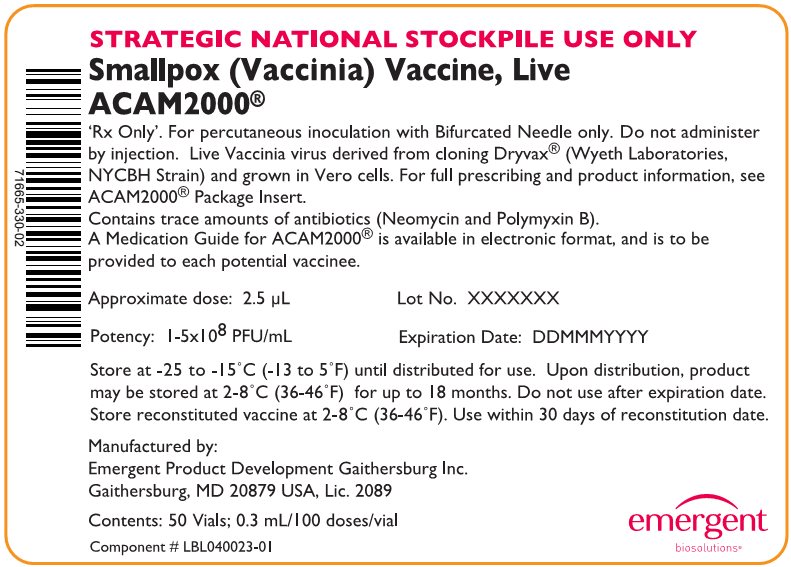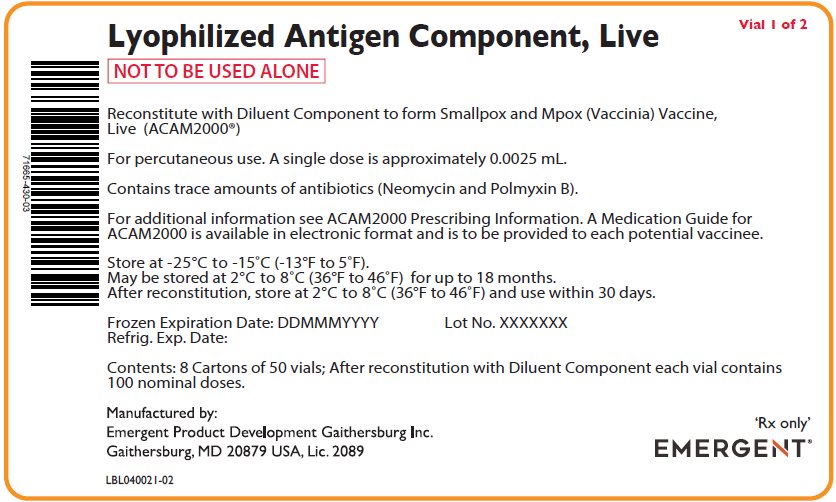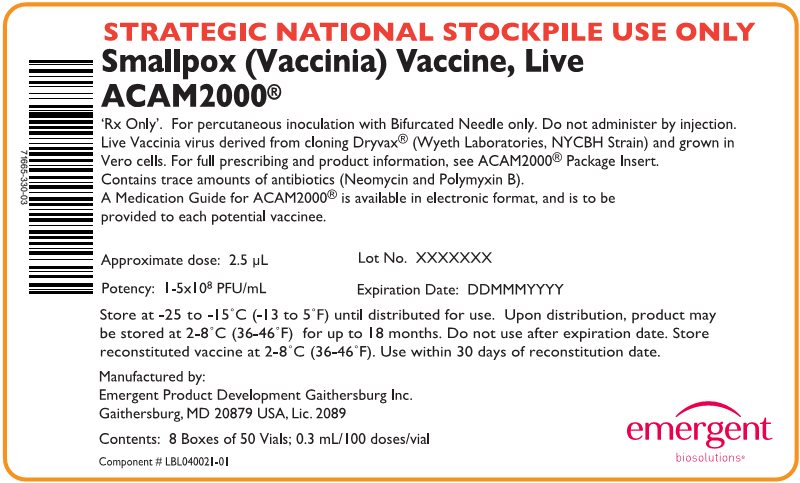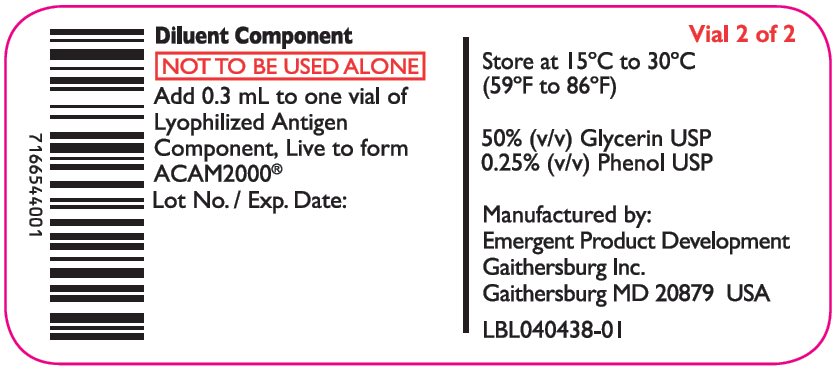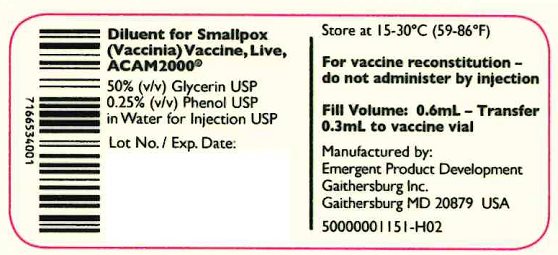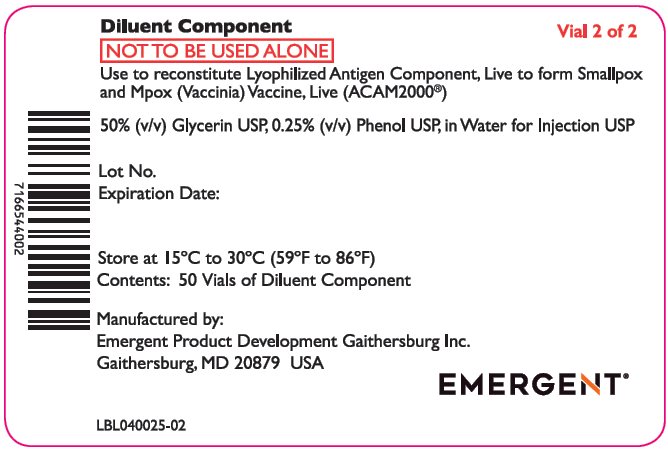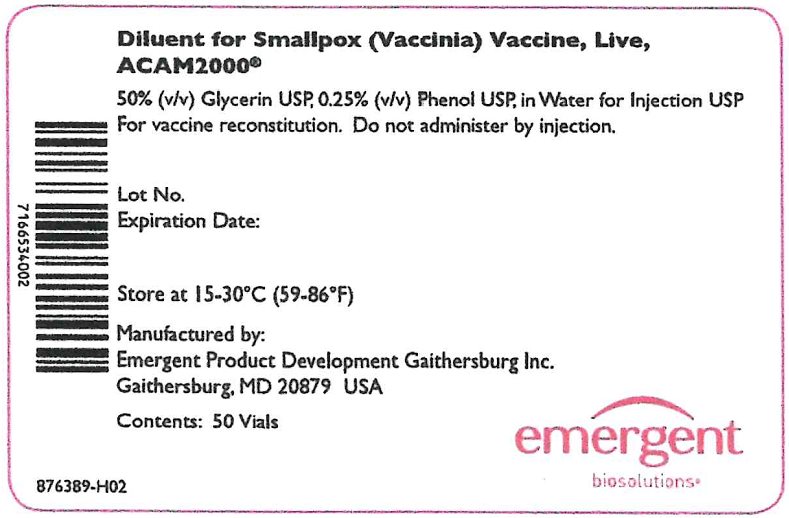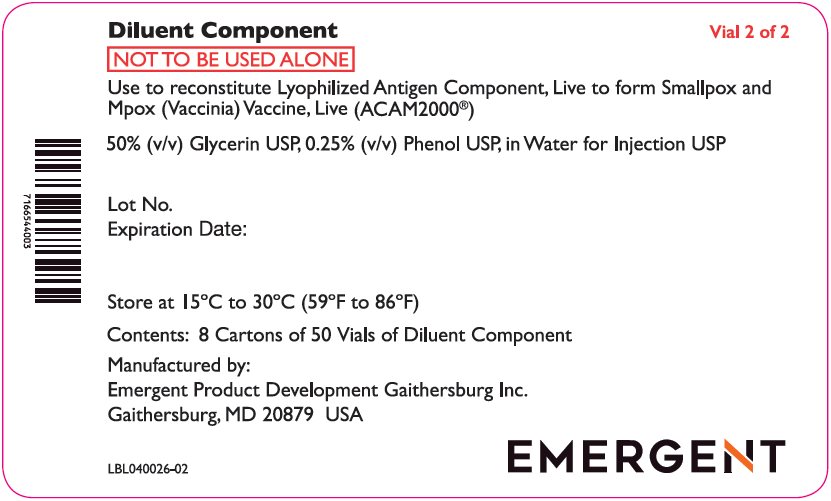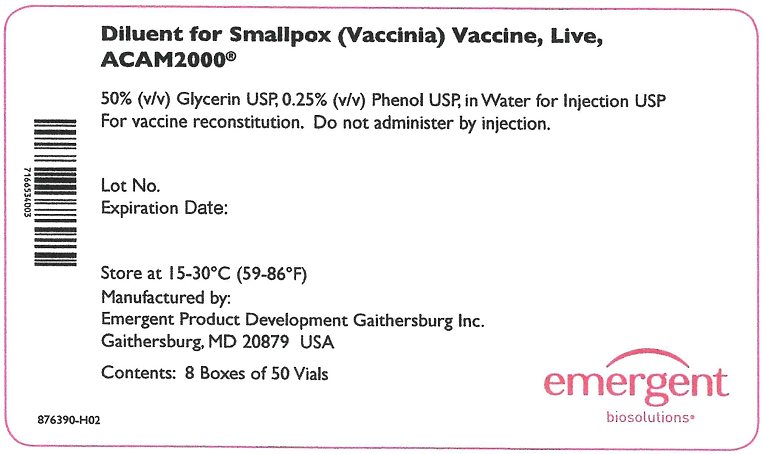 DRUG LABEL: ACAM2000
NDC: 71665-430 | Form: INJECTION, POWDER, LYOPHILIZED, FOR SOLUTION
Manufacturer: Emergent Product Development Gaithersburg Inc.
Category: other | Type: VACCINE LABEL
Date: 20250225

ACTIVE INGREDIENTS: VACCINIA VIRUS STRAIN NEW YORK CITY BOARD OF HEALTH LIVE ANTIGEN 100000000 [PFU]/1 mL
INACTIVE INGREDIENTS: ALBUMIN HUMAN 20 mg/1 mL; SODIUM CHLORIDE 6 mg/1 mL; MANNITOL 50 mg/1 mL

HIGHLIGHTS OF PRESCRIBING INFORMATION

These highlights do not include all the information needed to use ACAM2000 safely and effectively. See full prescribing information for ACAM2000.
ACAM2000® [Smallpox and Mpox (Vaccinia) Vaccine, Live]
For scarification suspension, for percutaneous use
Initial U.S. Approval: 2007

RECENT MAJOR CHANGES

Indications and Usage, mpox disease (1) 8/2024

WARNING: SERIOUS COMPLICATIONS

See full prescribing information for complete boxed warning.

Myocarditis and pericarditis (suspect cases observed at a rate of 5.7 per 1000 primary vaccinees (95% CI: 1.9-13.3)), encephalitis, encephalomyelitis, encephalopathy, progressive vaccinia, generalized vaccinia, severe vaccinial skin infections, erythema multiforme major (including STEVENS-JOHNSON SYNDROME), eczema vaccinatum resulting in permanent sequelae or death, accidental eye infection (ocular vaccinia) which can cause ocular complications that may lead to blindness, and fetal death, have occurred following either primary vaccination or revaccination with ACAM2000 or other live vaccinia virus vaccines that were used historically. These risks are increased in certain individuals and may result in severe disability, permanent neurological sequelae and/or death [see Warnings and Precautions (5)].

1 INDICATIONS AND USAGE

ACAM2000® is indicated for active immunization for the prevention of smallpox and mpox disease in individuals determined to be at high risk for smallpox or mpox infection. (1).

2 DOSAGE AND ADMINISTRATION

For percutaneous use by scarification. (2)

- Administer ACAM2000 only after being trained on the safe and effective administration of the vaccine. (2.4)
- A droplet of ACAM2000 is administered by scarification percutaneously using 15 jabs of a bifurcated needle. (2.4)
- The droplet (approximately 0.0025 mL) of reconstituted vaccine is picked up with a bifurcated needle by dipping needle into ACAM2000 vial. (2.4)
- See full prescribing information for instructions for vaccine preparation (2.2), administration including provision of the Medication Guide to vaccinees and instruction to vaccinees about vaccination site care (2.6) and interpretation of response to vaccination. (2.7)

3 DOSAGE FORMS AND STRENGTHS

- For scarification suspension. (3)
- ACAM2000 is supplied as a multiple dose vial of Lyophilized Antigen Component, Live to be reconstituted with the supplied Diluent Component. After reconstitution, a single dose of ACAM2000 is approximately 0.0025 mL. (3)

4 CONTRAINDICATIONS

- Individuals with severe immunodeficiency. These individuals may include persons who are undergoing bone marrow transplantation or persons with primary or acquired immunodeficiency states who require isolation. (4).

5 WARNINGS AND PRECAUTIONS

- Myocarditis and/or pericarditis, ischemic heart disease and non-ischemic dilated cardiomyopathy. (5.1, 5.2)
- Encephalitis, encephalomyelitis, encephalopathy, progressive vaccinia (vaccinia necrosum), generalized vaccinia, severe vaccinial skin infections, erythema multiforme major (including Stevens-Johnson syndrome), eczema vaccinatum, fetal vaccinia and fetal death. (5.1)
- Ocular vaccinia that may lead to blindness. (5.3)
- These risks, including risks of severe disability and/or death, are increased in vaccinees with:
  - Cardiac disease. (5.2)
  - Eye disease treated with topical steroids. (5.3)
  - Congenital or acquired immune deficiency disorders. (5.4)
  - History or presence of eczema and other skin conditions. (5.5)
  - Infants < 12 months of age. (5.6)
  - Pregnancy. (5.7)
- ACAM2000 is a live vaccinia virus that can be transmitted to persons who have close contact with the vaccinee and the risks in contacts are the same as those stated for vaccinees. (5.10)

6 ADVERSE REACTIONS

Common adverse reactions include inoculation site signs and symptoms, lymphadenitis, and constitutional symptoms, such as malaise, fatigue, fever, myalgia, and headache (6). These adverse reactions are less frequent in revaccinated persons than persons receiving the vaccine for the first time.
Inadvertent inoculation at other sites is the most frequent complication of vaccinia vaccination. The most common sites involved are the face, nose, mouth, lips, genitalia and anus.
Self-limited skin rashes not associated with vaccinia replication in skin, including urticaria and folliculitis, may occur following vaccination.

To report SUSPECTED ADVERSE REACTIONS, contact Emergent BioSolutions at 1-877-246-8472 and medicalinformation@ebsi.com or VAERS at 1-800-822-7967 and https://vaers.hhs.gov.

8 USE IN SPECIFIC POPULATIONS

- ACAM2000 may rarely cause fetal infection, usually resulting in stillbirth or death. (8.1)
- ACAM2000 live vaccinia virus may be transmitted from a lactating mother to her infant causing complications in the infant from inadvertent inoculation. (8.2)
- ACAM2000 may be associated with an increased risk of serious complications in children, especially in infants younger than 12 months. (8.4)

FULL PRESCRIBING INFORMATION

WARNING: SERIOUS COMPLICATIONS

- Suspected cases of myocarditis and/or pericarditis have been observed in healthy adult primary vaccinees (at an approximate rate of 5.7 per 1000, 95% CI: 1.9-13.3) receiving ACAM2000 [see Warnings and Precautions (5.1)].
- Encephalitis, encephalomyelitis, encephalopathy, progressive vaccinia, generalized vaccinia, severe vaccinial skin infections, erythema multiforme major (including STEVENS-JOHNSON SYNDROME), eczema vaccinatum resulting in permanent sequelae or death, and fetal death have occurred following either primary vaccination or revaccination with ACAM2000 or other live vaccinia virus vaccines that were used historically [see Warnings and Precautions (5)].
- Accidental eye infection (ocular vaccinia) may result in ocular complications including keratitis and corneal scarring that may lead to blindness [see Warning and Precautions (5.3)].
- These risks may result in severe disability, permanent neurological sequelae and/or death and are increased in individuals who:
  - Have cardiac disease or a history of cardiac disease
  - Have eye disease treated with topical steroids
  - Have congenital or acquired immune deficiency disorders, including individuals taking immunosuppressive medications
  - Have eczema or a history of eczema or other acute or chronic exfoliative skin conditions
  - Are less than 12 months of age
  - Are pregnant

ACAM2000 contains live vaccinia virus that can be transmitted to persons who have close contact with the vaccinee and the risks in contacts are the same as those for the vaccinee.

The risk for experiencing serious vaccination complications must be weighed against the risks for experiencing a potentially severe or fatal smallpox or mpox infection.

1 INDICATIONS AND USAGE

ACAM2000® is a vaccine indicated for active immunization for the prevention of smallpox and mpox disease in individuals determined to be at high risk for smallpox or mpox infection.

2 DOSAGE AND ADMINISTRATION

2.1 Route of Administration

Administer ACAM2000 only after being trained on the safe and effective administration of the vaccine by the percutaneous route (scarification).

Do not administer ACAM2000 by injection.

2.2 Vaccine Preparation

ACAM2000 is supplied as a multiple dose vial of Lyophilized Antigen Component, Live to be reconstituted with the supplied Diluent Component.

The Lyophilized Antigen Component, Live is supplied in cartons and vials labeled “Smallpox (Vaccinia) Vaccine, Live, ACAM2000.” The Diluent Component may be supplied in cartons and vials labeled “Diluent for Smallpox (Vaccinia) Vaccine, Live, ACAM2000.” Reconstitution instructions and storage following reconstitution are described below.

Reconstitution

Reconstitute the Lyophilized Antigen Component, Live only with 0.3 mL of the provided Diluent Component to form ACAM2000. Note: 0.3 mL of diluent is not the entire content of the vial of Diluent Component.

Remove the Lyophilized Antigen Component, Live vial from freezer or refrigerator and bring to room temperature before reconstitution.

Remove the flip cap seals of the Lyophilized Antigen Component, Live and Diluent Component vials and wipe with an isopropyl alcohol swab and allow to dry thoroughly.

Use aseptic technique and a sterile 1 mL syringe fitted with a 25 gauge x 5/8” needle (provided) to draw up 0.3 mL from the Diluent Component vial and transfer the entire content of the syringe to the Lyophilized Antigen Component, Live vial.

Gently swirl to mix, do not shake or invert the vial, and avoid product contact with the rubber stopper.

The reconstituted vaccine should be a clear to slightly hazy, colorless to straw-colored liquid free from extraneous matter. Parenteral drug products should be inspected visually for particulate matter and discoloration prior to administration, whenever solution and container permit. If particulate matter or discoloration is observed, do not use the vaccine and dispose of the vial as biohazardous material [see Dosage and Administration (2.5)].

After reconstitution, each vial contains 100 nominal doses of approximately 0.0025 mL each.

Storage following Reconstitution

After reconstitution, ACAM2000 may be administered within 8 hours if kept at 20°C to 25°C (68°F to 77°F). Store unused, reconstituted ACAM2000 in a refrigerator 2°C to 8°C (36°F to 46°F) for up to 30 days, after which the unused portion is to be discarded as a biohazardous material [see Dosage and Administration (2.5)]. Minimize exposure of reconstituted vaccine to room temperature during vaccination sessions by placing it in the refrigerator or on ice between patient administrations.

2.3 Preparation / Handling Precautions

Wear surgical or protective gloves when preparing and administering the vaccine to avoid contact of vaccine with skin, eyes or mucous membranes.

2.4 Vaccine Administration

Bring the reconstituted vaccine to room temperature prior to administration. Before administration, examine the vial contents to verify the absence of particulates and gently swirl, without allowing the product to contact the rubber stopper, if necessary to re-dissolve any precipitates that might have formed.

The site of vaccination is the upper arm over the insertion of the deltoid muscle.

No skin preparation should be performed unless the skin at the intended site of vaccination is obviously dirty, in which case an alcohol swab(s) may be used to clean the area. If alcohol is used, the skin must be allowed to dry thoroughly to prevent inactivation of the live vaccine virus by the alcohol.

Remove the vaccine vial cap. Remove bifurcated needle from individual wrapping. Submerge bifurcated end of needle in reconstituted vaccine solution. The needle will pick up a droplet of vaccine (approximately 0.0025 mL) within the fork of the bifurcation. Use aseptic technique, i.e., do not insert the upper part of the needle that has been in contact with fingers into the vaccine vial, and never redip the needle into the vaccine vial if the needle has touched skin.

Deposit the droplet of vaccine onto clean, dry skin of the arm prepared for vaccination. The needle is held between thumb and first finger perpendicular to the skin. The wrist of the vaccinator’s hand holding the needle rests against the vaccine recipient’s arm. Rapidly make 15 jabs of the needle perpendicular to the skin through the vaccine droplet to puncture the skin, within a diameter of about 5 mm. The jabs should be vigorous enough so that a drop of blood appears at the vaccination site.

Wipe any excess droplets of vaccine and blood off the skin using a dry gauze pad and discard in a biohazard container. Discard the needle in a biohazard sharps container [see Dosage and Administration (2.5)]. Close the vaccine vial by reinserting the rubber cap and return to a refrigerator or place on ice unless it will be used immediately to vaccinate another individual.

2.5 Disposal

Discard the Lyophilized Antigen Component, Live vial (including any unused reconstituted vaccine), its stopper, the syringe and needle used for reconstitution, the bifurcated needle used for administration, and any gauze or cotton that came in contact with the vaccine in leak-proof, puncture-proof biohazard containers. Dispose of these containers appropriately.

2.6 Care of the Vaccination Site

Ensure each vaccine recipient has the FDA-approved Medication Guide, which includes instructions for care of the vaccination site.

Cover vaccination site with gauze and secure it loosely with first aid adhesive tape. The gauze provides a barrier to protect against spread of the vaccinia virus. If the vaccinee is involved in direct patient care, the gauze may be covered with a semipermeable (semi-occlusive) dressing as an additional barrier. A semipermeable dressing is one that allows for the passage of air but does not allow for the passage of fluids.

Do not use a bandage that blocks air from the vaccination site. This may cause the skin at the vaccination site to soften and wear away.

Wash hands with soap and warm water or with alcohol-based hand rubs such as gels or foams after direct contact with the vaccination site, the gauze and semipermeable dressing, clothes, towels or sheets that might be contaminated with virus from the vaccination site. This is vital in order to remove any virus from your hands and prevent contact spread.

Throw away the contaminated gauze and semipermeable dressing in a sealed plastic bag. A small amount of bleach can be added to the bag to kill the vaccine virus.

Wash separately clothing, towels, bedding or other items that may have come in direct contact with the vaccination site or drainage from the site, using hot water with detergent and/or bleach. Wash hands afterwards.

Do not put salves or ointments on the vaccination site.

2.7 Interpreting Vaccination Response

Primary Vaccinees

In an individual vaccinated for the first time (primary vaccination; vaccinia-naïve), the expected response to vaccination is the development of a major cutaneous reaction (characterized by a pustule) at the site of inoculation. The lesion evolves gradually, with appearance of a papule at the site of vaccination after 2-5 days. The papule becomes vesicular surrounded by a red areola, then pustular, and reaches its maximum size at 8-10 days after vaccination; the pustule dries and forms a scab (See Figure 1). In primary vaccinees, scab separation and re-epithelialization occurs 3-6 weeks after vaccination, leaving a pitted scar. Formation of a major cutaneous reaction by day 6-11 is evidence of a successful ‘take’ and acquisition of protective immunity. An equivocal reaction is any reaction that is not a major reaction and indicates a non-take (vaccination failure) due to impotent vaccine or inadequate vaccination technique.

Individuals who are not successfully vaccinated (i.e., vaccination failures) after primary vaccination may be revaccinated again in an attempt to achieve a satisfactory take. The vaccination procedures should be checked, and vaccination repeated with vaccine from another vial or vaccine lot, employing the same technique described in section 2.4 [see Dosage and Administration (2.4)]. If a repeat vaccination is conducted using vaccine from another vial or vaccine lot fails to produce a major reaction, healthcare providers should consult the Centers for Disease Control and Prevention (CDC) Emergency Operations Center (EOC) at 770-488-7100 and their state or local health department before giving another vaccination.

Previously Vaccinated Individuals (Revaccination)

Based on data from Study 2 [see Adverse Reactions (6.1)], successful vaccination in an individual previously exposed to vaccine (vaccinia-experienced) is confirmed when a major cutaneous reaction is observed 6 to 8 days post-vaccination. A major cutaneous reaction at the vaccination site heals through the same stages as described in primary vaccinees and scab separation may occur earlier in revaccinated individuals than in primary vaccinees (Figure 2). However, any prior vaccination may modify (reduce) the cutaneous response upon revaccination (Figure 2) such that the absence of a cutaneous response does not necessarily indicate vaccination failure. Vaccinia-experienced individuals who do not have a cutaneous response on revaccination do not require revaccination to try to elicit a cutaneous response.

Figure 1 Progression of Major Cutaneous Reaction After Primary Vaccination (1)

Figure 2 Progression of Major Cutaneous Reaction After Revaccination (1)

2.8 Revaccination

The U.S. Centers for Disease Control and Prevention (CDC) has recommendations for revaccination of laboratory and health care personnel at risk for occupational exposure to variola and mpox viruses (2).

3 DOSAGE FORMS AND STRENGTHS

For scarification suspension. ACAM2000 is supplied as a multiple dose vial of Lyophilized Antigen Component, Live to be reconstituted with the supplied Diluent Component. After reconstitution, a single dose of ACAM2000 is approximately 0.0025 mL.

4 CONTRAINDICATIONS

Severe Immune Deficiency

Do not administer ACAM2000 to individuals with severe immunodeficiency. These individuals may include individuals who are undergoing bone marrow transplantation or individuals with primary or acquired immunodeficiency who require isolation.

5 WARNINGS AND PRECAUTIONS

5.1 Serious Complications

Serious complications that may follow either primary or revaccination with ACAM2000 include: myocarditis and/or pericarditis, encephalitis, encephalomyelitis, encephalopathy, progressive vaccinia (vaccinia necrosum), generalized vaccinia, severe vaccinial skin infections, erythema multiforme major (including Stevens-Johnson syndrome), eczema vaccinatum, accidental eye infection (ocular vaccinia) which can cause ocular complications including keratitis and corneal scarring that may lead to blindness, and fetal death in pregnant women. These complications may rarely lead to severe disability, permanent neurological sequalae and death. Based on ACAM2000 clinical trials, symptoms of suspected myocarditis or pericarditis (such as chest pain, raised troponin/cardiac enzymes, or ECG abnormalities) occurred in 5.7 per 1000 primary vaccinations. This finding includes cases of acute symptomatic or asymptomatic myocarditis or pericarditis or both. Historically, death following vaccination with live vaccinia virus is a rare event; approximately 1 death per million primary vaccinations and 1 death per 4 million revaccinations have occurred after vaccination with live vaccinia virus. Death is most often the result of sudden cardiac death, post-vaccinial encephalitis, progressive vaccinia, or eczema vaccinatum. Death has also been reported in unvaccinated contacts accidentally infected by individuals who have been vaccinated.

Incidence of Serious Complications in 1968 U.S. Surveillance Studies

Estimates of the risks of occurrence of serious complications after primary vaccination and revaccination, based on safety surveillance studies conducted when live vaccinia virus smallpox vaccine (i.e., New York City Board of Health strain, Dryvax) was routinely recommended, are as follows:

Table 1 Rates of Reported Complications(a) Associated with Primary Vaccinia Vaccinations (Cases/Million Vaccinations)(b)
Age (yrs) | <1 | 1-4 | 5-19 | ≥20 | Overall rates(h)
Inadvertent inoculation(c) | 507.0 | 577.3 | 371.2 | 606.1 | 529.2
Generalized vaccinia | 394.4 | 233.4 | 139.7 | 212.1 | 241.5
Eczema vaccinatum | 14.1 | 44.2 | 34.9 | 30.3 | 38.5
Progressive vaccinia(d) | --(g) | 3.2 | --(g) | --(g) | 1.5
Postvaccinial encephalitis | 42.3 | 9.5 | 8.7 | --(g) | 12.3
Death(e) | 5 | 0.5 | 0.5 | unknown | --
Total(f) | 1549.3 | 1261.8 | 855.9 | 1515.2 | 1253.8
a. See article for descriptions of complications.
b. Adapted from (3) and (4).
c. Referenced as accidental implantation.
d. Referenced as vaccinia necrosum.
e. Death from all complications.
f. Rates of overall complications by age group include complications not provided in this table, including severe local reactions, bacterial superinfection of the vaccination site, and erythema multiforme.
g. No instances of this complication were identified during the 1968 ten (10) state survey.
h. Overall rates for each complication include persons of unknown age.

Table 2 Rates of Reported Serious Complications(a) Associated with Vaccinia Revaccinations (Cases/Million Vaccinations)(b)
Age (yrs) | <1 | 1-4 | 5-19 | ≥20 | Overall rates(b)
Inadvertent inoculation(c) | (g) | 109.1 | 47.7 | 25.0 | 42.1
Generalized vaccinia | (g) | (g) | 9.9 | 9.1 | 9.0
Eczema vaccinatum | (g) | (g) | 2.0 | 4.5 | 3.0
Progressive vaccinia(d) | (g) | (g) | (g) | 6.8 | 3.0
Postvaccinial encephalitis | (g) | (g) | (g) | 4.5 | 2.0
Death(e) | -- | -- | -- | -- | --
Total(f) | (g) | 200.0 | 85.5 | 113.6 | 108.2
See Table 1 for explanation of footnotes.

Incidence of Serious Complications and Emergence of Myocarditis and/or Pericarditis in 2002-2005

Data on the incidence of adverse events among U.S. military personnel and civilian first responders vaccinated with Dryvax, a formerly licensed live vaccinia virus smallpox vaccine, during vaccination programs initiated in December 2002 are shown below in Table 3.

The incidence of preventable adverse events (eczema vaccinatum, contact transmission, and auto-inoculation) were notably lower in these programs when compared with data collected in the 1960s; presumably because of better vaccination screening procedures and routine use of protective bandages over the inoculation site. Myocarditis and pericarditis were not commonly reported following smallpox vaccination in the 1960s but emerged as a more frequent event based on more active surveillance in the military and civilian programs.

Table 3 Serious Adverse Events in 2002-2005^5
Adverse event | Na | Incidence/ million | Nb | Incidence/million
Myo/pericarditis | 86 | 117.71 | 21 | 519.52
Post-vaccinial encephalitis | 1 | 1.37 | 1 | 24.74
Eczema vaccinatum | 0 | 0.00 | 0 | 0.00
Generalized vaccinia | 43 | 58.86 | 3 | 74.22
Progressive vaccinia | 0 | 0.00 | 0 | 0.00
Fetal vaccinia | 0 | 0.00 | 0 | 0.00
Contact transmission | 52 | 71.18 | 0 | 0.00
Auto-inoculation (non-ocular) | 62 | 84.86 | 20 | 494.78
Ocular vaccinia | 16 | 21.90 | 3 | 74.22
a. Department of Defense program (n=730,580) as of Jan05 where 71% primary vaccination; 89% male; median age 28.5 years
b. Department of Health and Human Services program (n=40, 422) as of Jan04 where 36% primary vaccination; 36% male; median age 47.1 years

Myocarditis and Pericarditis in the ACAM2000 Clinical Trial Experience

In clinical trials involving 2983 subjects who received ACAM2000 and 868 subjects who received Dryvax, ten (10) cases of suspected myocarditis [0.2% (7 of 2983) ACAM2000 subjects and 0.3% (3 of 868) Dryvax subjects] were identified. The mean time to onset of suspected myocarditis and/or pericarditis from vaccination was 11 days, with a range of 9 to 20 days. All subjects who experienced these cardiac events were naïve to vaccinia. Of the 10 subjects, 2 were hospitalized. None of the remaining 8 cases required hospitalization or treatment with medication. Of the 10 cases, 8 were sub-clinical and were detected only by ECG abnormalities with or without associated elevations of cardiac troponin I. All cases were resolved by 9 months, with the exception of one female subject in the Dryvax group, who had persistent borderline abnormal left ventricular ejection fraction on echocardiogram. The best estimate of risk for myocarditis and pericarditis was derived from the Phase 3 ACAM2000 clinical trials where there was active monitoring for the potential of myocarditis and pericarditis. Among vaccinees naïve to vaccinia, 8 cases of suspected myocarditis and pericarditis were identified across both vaccine groups, for a total incidence rate of 6.9 per 1000 vaccinees (8 of 1,162). The incidence rate for the ACAM2000 vaccine group was 5.7 (95% CI: 1.9-13.3) per 1000 vaccinees (5 of 873 vaccinees) and for the Dryvax group was 10.4 (95% CI: 2.1-30.0) per 1000 vaccinees (3 of 289 vaccinees). No cases of myocarditis and/or pericarditis were identified in 1819 vaccinia-experienced subjects. The long-term outcome of myocarditis and pericarditis following ACAM2000 vaccination is currently unknown.

5.2 Cardiac Disease

Information on risks of myocarditis and pericarditis is presented in Section 5.1 [see Warnings and Precautions (5.1)].

Ischemic cardiac events, including fatal events, and non-ischemic, dilated cardiomyopathy have been reported following ACAM2000 and other live vaccinia virus vaccines that were used historically. The relationship of these events to vaccination is unknown.

There may be increased risks of adverse events with ACAM2000 in persons with known cardiac disease, including those diagnosed with previous myocardial infarction, angina, congestive heart failure, cardiomyopathy, chest pain or shortness of breath with activity, stroke or transient ischemic attack, or other heart conditions. In addition, individuals who have been diagnosed with 3 or more of the following risk factors for ischemic coronary disease may have increased risks: 1) high blood pressure; 2) elevated blood cholesterol; 3) diabetes mellitus or high blood sugar; 4) first degree relative (for example mother, father, brother, or sister) who had a heart condition before the age of 50; or 5) smoke cigarettes.

5.3 Ocular Complications

Accidental infection of the eye (ocular vaccinia) may result in ocular complications, including keratitis and corneal scarring that may lead to blindness. Patients who are using corticosteroid eye drops may be at increased risk of ocular complications with ACAM2000.

5.4 Presence of Congenital or Acquired Immune Deficiency Disorders

Severe localized or systemic infection with vaccinia (progressive vaccinia) may occur in persons with weakened immune systems, including patients with leukemia, lymphoma, organ transplantation, generalized malignancy, HIV/AIDS, cellular or humoral immune deficiency, radiation therapy, or treatment with antimetabolites, alkylating agents, high-dose corticosteroids (>10 mg prednisone/day or equivalent for ≥2 weeks), or other immunomodulatory drugs. ACAM2000 is contraindicated in individuals with severe immunodeficiency [see Contraindications (4)]. Close contacts of vaccinees (including sexual contacts) who have these conditions may be at increased risk because live vaccinia virus can be shed and be transmitted to close contacts.

5.5 History or Presence of Eczema and Other Skin Conditions

Persons with eczema of any description such as: atopic dermatitis, neurodermatitis, and other eczematous conditions, regardless of severity of the condition, or persons who have a history of these conditions at any time in the past, are at higher risk of developing eczema vaccinatum. Vaccinees with close contacts who have eczematous conditions, may be at increased risk because live vaccinia virus can shed and be transmitted to these close contacts. Vaccinees with other active acute, chronic or exfoliative skin disorders (including burns, impetigo, varicella zoster, acne vulgaris with open lesions, Darier’s disease, psoriasis, seborrheic dermatitis, erythroderma, pustular dermatitis, etc.), or vaccinees with household contacts having such skin disorders might also be at higher risk for eczema vaccinatum.

5.6 Infants < 12 months of Age

Based on data from historical use of other live vaccinia virus vaccines, the risk of serious adverse reactions following vaccination with ACAM2000 is higher in infants (<12 months of age). Vaccinated persons who have close contact with infants must take precautions to avoid inadvertent transmission of ACAM2000 live vaccinia virus to infants.

5.7 Pregnancy

ACAM2000 has not been studied in pregnant women. Based on data from historical use of other live vaccinia virus vaccines, ACAM2000 can cause fetal vaccinia and fetal death. If ACAM2000 is administered during pregnancy or within 6 weeks before becoming pregnant, the vaccinee should be apprised of the potential hazard to the fetus [see Use in Specific Populations (8.1)]. Vaccinees should be counseled to avoid becoming pregnant (or getting their partner pregnant) for 6 weeks after vaccination and until the vaccination site has healed.

Pregnant women who are close contacts of vaccinees may be at risk of adverse fetal outcomes because ACAM2000 live vaccinia virus can be transmitted from vaccinees. [see Use in Specific Populations (8.1)].

5.8 Severe Allergic Reactions

Appropriate medical treatment must be immediately available to manage potential anaphylactic reactions following administration of ACAM2000.

Persons who experienced a severe allergic reaction following a previous dose of ACAM2000 or following exposure to any ingredient of ACAM2000, including neomycin or polymyxin B, may be at increased risk for severe allergic reactions.

5.9 Management of ACAM2000 Complications

The CDC can assist physicians in the diagnosis and management of patients with suspected complications of ACAM2000 vaccination. Vaccinia immune globulin intravenous (human) (CNJ-016®) is indicated for the treatment of certain complications due to vaccinia vaccination. If CNJ-016 and/or other antivirals are needed or additional information is required, physicians should contact the CDC Emergency Operations Center (EOC) at 1-800-232-4636 (CDC-INFO).

5.10 Prevention of Transmission of Live Vaccinia Virus

The most important measure to prevent inadvertent auto-inoculation and contact transmission from ACAM2000 vaccination is thorough hand washing after changing the bandage or after any other contact with the vaccination site.

Individuals susceptible to adverse effects of vaccinia virus, i.e., those with cardiac disease, eye disease, immunodeficiency states, including HIV infection, eczema, pregnant women and infants, should be identified and measures should be taken to avoid contact between those individuals and persons with active vaccination lesions.

Recently vaccinated healthcare workers should avoid contact with patients, particularly those with immunodeficiencies, until the scab has separated from the skin at the vaccination site. However, if contact with patients is unavoidable, vaccinated healthcare workers should ensure the vaccination site is well covered and follow good hand-washing technique. In this setting, the loose gauze held in place with first aid tape may be covered with a semipermeable (semi-occlusive) dressing as an additional barrier. Semipermeable polyurethane dressings are effective barriers to shedding of vaccinia. However, exudate may accumulate beneath the dressing, and care must be taken to prevent viral spread when the dressing is changed. In addition, accumulation of fluid beneath the dressing may increase skin maceration at the vaccination site. Accumulation of exudate may be decreased by first covering the vaccination with dry gauze, then applying the dressing over the gauze.

The gauze and dressing should be changed every 1 to 3 days [see Patient Counseling Information (17)].

5.11 Blood and Organ Donation

Blood and organ donation should be avoided for 6 weeks following vaccination with ACAM2000.

5.12 Limitations of Vaccine Effectiveness

ACAM2000 may not protect all recipients.

6 ADVERSE REACTIONS

The following adverse reactions are discussed in greater detail in other sections of the labeling:

- Encephalitis, encephalomyelitis, encephalopathy, progressive vaccinia (vaccinia necrosum), generalized vaccinia, severe vaccinial skin infections, erythema multiforme major (including Stevens-Johnson syndrome) and eczema vaccinatum. Severe disability, permanent neurological sequelae, and/or death may occur. Death of unvaccinated individuals who have contact with vaccinated individuals. [See Warnings and Precautions (5.1)].
- Myocarditis and/or pericarditis, ischemic heart disease and non-ischemic, dilated cardiomyopathy [see Warnings and Precautions (5.1)].
- Ocular complications [see Warnings and Precautions (5.3)].

6.1 Clinical Trials Experience

The following information regarding the safety of ACAM2000 was derived from three sources: 1) ACAM2000 clinical trial experience (Phase 1, 2 and 3 clinical trials), 2) data compiled during the era of routine smallpox vaccination using other New York City Board of Health (NYCBH) vaccinia vaccines and 3) adverse event data obtained during military and civilian smallpox vaccination programs (2002-2005) that used Dryvax, a formerly licensed live vaccinia virus smallpox vaccine.

- General Disorders and Administration Site Conditions: In the ACAM2000 clinical studies 97% and 92% of vaccinia-naïve and vaccinia-experienced subjects, respectively, experienced one or more adverse event. Common events included injection site reactions (erythema, pruritus, pain and swelling) and constitutional symptoms (fatigue, malaise, feeling hot, rigors and exercise tolerance decreased). Across all ACAM2000 studies 10% of vaccinia-naïve and 3% of vaccinia-experienced subjects experienced at least one severe adverse event (defined as interfering with normal daily activities).
- Nervous System Disorders: Overall, 50% and 34% of vaccinia-naïve subjects and vaccinia-experienced subjects, respectively, reported headaches in ACAM2000 studies. There have been reports of headache following smallpox vaccination which required hospitalization. Although <1% of the subjects in the ACAM2000 program experienced severe headaches, none required hospitalization.
  Neurological adverse events assessed among the 2002 - 2005 military (n=590,400) and DHHS (n=64,600) programs temporally associated with smallpox vaccination included headache (95 cases), non-serious limb paresthesias (17 cases) or pain (13 cases) and dizziness or vertigo (13 cases). Serious neurologic adverse events included 13 cases of suspected meningitis, 3 cases of suspected encephalitis or myelitis, 11 cases of Bell palsy, 9 seizures (including 1 death), and 3 cases of Guillain-Barre syndrome. Among these 39 events, 27 (69%) occurred in primary vaccinees and all but 2 occurred within 12 days of vaccination. There have also been cases of photophobia following smallpox vaccination, some of which required hospitalization.
- Musculoskeletal and Connective Tissue Disorders: Across all ACAM2000 studies, severe, vaccine-related myalgia was seen in 1% of vaccinia-naïve subjects and <1% of vaccinia-experienced subjects. Other adverse events included back pain, arthralgia and pain in extremity and none occurred with a frequency of more than 2% in either the vaccinia-naïve or vaccinia-experienced populations.
- Blood and Lymphatic System Disorders: The only adverse event occurring at ≥5% in the ACAM2000 studies were lymph node pain and lymphadenopathy. The incidence of severe lymph node pain and lymphadenopathy was <1%.
- Gastrointestinal (GI) Disorders: Commonly reported GI disorders among subjects who received ACAM2000 included nausea and diarrhea (14%), constipation (6%), and vomiting (4%). Severe abdominal pain, nausea, vomiting, constipation, diarrhea and toothache accounted for all the severe adverse events reported and occurred in <1% of subjects.
- Skin and Subcutaneous Tissue Disorders: Erythema and rash were noted in 18% and 8% of subjects respectively. In ACAM2000 subjects 1% of vaccinia-naïve and <1% of vaccinia-experienced subjects experienced at least one severe adverse event. With the exception of one case of contact dermatitis and one case of urticaria, erythema and rash accounted for all severe events.
  Generalized rashes (erythematous, papulovesicular, urticarial, folliculitis, nonspecific) are not uncommon following smallpox vaccination and are presumed to be hypersensitivity reactions occurring among persons without underlying illnesses. These rashes are generally self-limited and require little or no therapy, except among patients whose conditions appear to be toxic or who have serious underlying illnesses.
  Inadvertent inoculation at other body sites is the most frequent complication of vaccinia vaccination, usually resulting from autoinoculation of the vaccine virus transferred from the site of vaccination. The most common sites involved are the face, nose, mouth, lips, genitalia and anus. Accidental infection of the eye (ocular vaccinia) may result in ocular complications including, but not limited to, keratitis and corneal scarring that may lead to blindness.
  Major cutaneous reactions at the site of inoculation, characterized by large area of erythema and induration and streaking inflammation of draining lymphatics may resemble cellulitis. Benign and malignant lesions have been reported to occur at the smallpox vaccination site.

Two randomized, controlled, multi-center Phase 3 trials enrolled 2244 subjects that received ACAM2000 and 737 that received a comparison formerly licensed live vaccinia virus vaccine, Dryvax. Study 1 was conducted in male (66% and 63% for ACAM2000 and Dryvax, respectively) and female (34% and 37% for ACAM2000 and Dryvax, respectively) subjects who previously had not been vaccinated with smallpox vaccine (i.e., vaccinia-naïve subjects).

The majority of subjects were Caucasian (76% and 71% for ACAM2000 and Dryvax, respectively) and the mean age was 23 in both groups with an age range from 18-30 years. Study 2 was conducted in male (50% and 48% for ACAM2000 and Dryvax, respectively) and female (50% and 52% for ACAM2000 and Dryvax, respectively) subjects who had been vaccinated with smallpox vaccine >10 years previously (i.e., vaccinia-experienced subjects). The majority of subjects were Caucasian (78% for both groups) and the mean age was 49 years in both groups with an age range of 31 to 84 years.

Common Adverse Reactions Reported in ACAM2000 Clinical Program

Adverse reactions reported by ≥5% of subjects in either the ACAM2000 or the comparison vaccine group during Phase 3 studies are presented by type of adverse reactions, by baseline vaccination status (vaccinia-naïve versus vaccinia-experienced) and by vaccine group. Severe vaccine-related adverse reactions, defined as interfering with normal daily activities, in vaccinia-naïve subjects were reported by 10% of subjects in the ACAM2000 group and 13% in the comparison group. In the vaccinia-experienced subjects, the incidence of severe vaccine-related adverse reactions was 4% for the ACAM2000 groups and 6% for the comparison group.

Table 4 Adverse Reactions by Preferred Term, Categorized by MedDRA System Organ Class, Reported by ≥5% of Subjects in ACAM2000 or Dryvax
Vaccine | ACAM2000 N=873 n (%) | Dryvax N=289 n (%) | ACAM2000 N=1371 n (%) | Dryvax N=448 n (%)
Prior Vaccination Status | Vaccinia-Naïve Subjects | Vaccinia-Naïve Subjects | Vaccinia-Experienced Subjects | Vaccinia-Experienced Subjects
At least 1 adverse reaction | 864 (99) | 288 (100) | 1325 (97) | 443 (99)
Blood and lymphatic system disorders | 515 (59) | 204 (71) | 302 (22) | 133 (30)
Lymph node pain | 494 (57) | 199 (69) | 261 (19) | 119 (27)
Lymphadenopathy | 72 (8) | 35 (12) | 78 (6) | 29 (6)
Gastrointestinal disorders | 273 (31) | 91 (31) | 314 (23) | 137 (31)
Nausea | 170 (19) | 65 (22) | 142 (10) | 63 (14)
Diarrhea | 144 (16) | 34 (12) | 158 (12) | 77 (17)
Constipation | 49 (6) | 9 (3) | 88 (6) | 31 (7)
Vomiting | 42 (5) | 10 (3) | 40 (3) | 18 (4)
General disorders and administration site conditions | 850 (97) | 288 (100) | 1280 (93) | 434 (97)
Injection site pruritus | 804 (92) | 277 (96) | 1130 (82) | 416 (93)
Injection site erythema | 649 (74) | 229 (79) | 841 (61) | 324 (72)
Injection site pain | 582 (67) | 208 (72) | 505 (37) | 209 (47)
Fatigue | 423 (48) | 161 (56) | 468 (34) | 184 (41)
Injection site swelling | 422 (48) | 165 (57) | 384 (28) | 188 (42)
Malaise | 327 (37) | 122 (42) | 381 (28) | 147 (33)
Feeling hot | 276 (32) | 97 (34) | 271 (20) | 114 (25)
Rigors | 185 (21) | 66 (23) | 171 (12) | 76 (17)
Exercise tolerance decreased | 98 (11) | 35 (12) | 105 (8) | 50 (11)
Musculoskeletal and connective tissue disorders | 418 (48) | 153 (53) | 418 (30) | 160 (36)
Myalgia | 404 (46) | 147 (51) | 374 (27) | 148 (33)
Nervous system disorders | 444 (51) | 151 (52) | 453 (33) | 174 (39)
Headache | 433 (50) | 150 (52) | 437 (32) | 166 (37)
Respiratory, thoracic, and mediastinal disorders | 134 (15) | 40 (14) | 127 (9) | 42 (9)
Dyspnea | 39 (4) | 16 (6) | 41 (3) | 18 (4)
Skin and subcutaneous tissue disorders | 288 (33) | 103 (36) | 425 (31) | 139 (31)
Erythema | 190 (22) | 69 (24) | 329 (24) | 107 (24)
Rash | 94 (11) | 30 (10) | 80 (6) | 29 (6)
Note: With the exception of lymphadenopathy, all reactions were listed on a checklist included in subject diaries; therefore, they should be considered solicited. Lymphadenopathy was identified upon patient examination and recorded during a structured interview. In addition to reactions listed above, the following were also included as part of the checklist: chest pain and heart palpitations, but these reactions did not occur in ≥5% of subjects.

6.2 Postmarketing Experience

The following adverse reactions have been identified in the postmarketing data for ACAM2000. Because these reactions are reported voluntarily from a population of uncertain size, it is not always possible to reliably estimate their frequency or establish a causal relationship to vaccine exposure.

- Cardiac Disorders: Myopericarditis
- Immune System Disorders: Hypersensitivity, Satellite lesions
- Infections and Infestations: Secondary transmission, Generalised Vaccinia, Eczema Vaccinatum, Encephalomyelitis, Superinfection
- Nervous System Disorders: Encephalopathy
- Skin and subcutaneous tissue disorders: Rash papular, Erythema multiforme, Stevens-Johnson Syndrome

7 DRUG INTERACTIONS

Interference with Laboratory Tests

During the first 6 weeks after vaccination, ACAM2000 may induce false-positive tests for syphilis. Positive rapid plasma reagin (RPR) tests results should be confirmed using a more specific test, such as the fluorescent treponemal antibody absorption (FTA-ABS) assay.

ACAM2000 may induce temporary false-negative results for the tuberculin skin test (purified protein derivative [PPD]) and possibly, blood tests for tuberculosis. Tuberculin testing should be delayed, if possible, for 6 weeks following smallpox vaccination.

8 USE IN SPECIFIC POPULATIONS

8.1 Pregnancy

Pregnancy Exposure Registry

There is a pregnancy exposure registry that monitors pregnancy outcomes in women exposed to ACAM2000 during pregnancy. Healthcare providers, state health departments, and other public health staff should report to the National Smallpox Vaccine in Pregnancy Registry (NSVIPR) all pregnant women who, from 42 days prior to conception onward, received ACAM2000 or had close contact with a person who received ACAM2000 within the previous 28 days. Civilian women should contact their healthcare provider or state health department for help enrolling in the registry. All civilian and military cases should be reported to the DoD, telephone 619-553-9255, Defense Switched Network (DSN) 553-9255, fax 619-767-4806 or e-mail usn.nhrc-VaccineRegistry@health.mil.

Risk Summary

All pregnancies have a risk of birth defect, loss, or other adverse outcomes. In the U.S. general population, the estimated background risk of major birth defects and miscarriage in clinically recognized pregnancies is 2% to 4% and 15% to 20%, respectively.

ACAM2000 has not been studied in pregnant women. Based on data from historical use of other live vaccinia virus vaccines, ACAM2000 can cause fetal harm when administered to a pregnant woman (see below in Fetal/Neonatal Adverse Reactions).

Clinical Considerations

ACAM2000 is not recommended for administration to pregnant women in non-emergency situations. If ACAM2000 is used during pregnancy or within 6 weeks before becoming pregnant, or if the vaccinee lives in the same household with or has close contact with a pregnant woman, the pregnant individual should be apprised of the potential hazard to the fetus [see Warnings and Precautions (5.7) and Patient Counselling Information (17)].

Disease-Associated Maternal and/or Embryo/Fetal Risk

Disease caused by smallpox (variola virus) can cause severe illness during pregnancy. Adverse pregnancy outcomes including spontaneous abortion and stillbirth have occurred after smallpox and mpox maternal infections.

Fetal/Neonatal Adverse Reactions

Congenital infection, principally occurring during the first trimester, was observed after vaccination with live vaccinia smallpox vaccines during the era of routine smallpox vaccination. Generalized vaccinia of the fetus, early delivery of a stillborn infant, and perinatal death have been reported from the historical experience with other live vaccinia smallpox vaccines.

8.2 Lactation

Risk Summary

ACAM2000 has not been studied in lactating women.

It is not known whether ACAM2000 is excreted in human milk. No human or animal data are available to assess the effects of ACAM2000 on the breastfed infant or on milk production/excretion.

The developmental and health benefits of breastfeeding should be considered along with the mother’s clinical need for ACAM2000 and any potential adverse effects on the breastfed child from ACAM2000 or from the underlying maternal condition. For preventive vaccines, the underlying condition is susceptibility to disease prevented by the vaccine.

Clinical Considerations

Persons vaccinated with ACAM2000 and who have close contact with infants (e.g., breastfeeding) must take precautions to avoid inadvertent transmission of live vaccinia virus to infants, which may result in serious complications [see Warnings and Precautions (5.6)].

8.3 Females and Males of Reproductive Potential

Contraception

An individual vaccinated with ACAM2000 should be counseled to avoid becoming pregnant (or getting their partner pregnant) for 6 weeks after vaccination.

8.4 Pediatric Use

ACAM2000 has not been studied in the pediatric population. The safety and effectiveness of ACAM2000 in all pediatric age groups is based on the safety and effectiveness of ACAM2000 in adults, historical data on safety and effectiveness of live vaccinia virus smallpox vaccines in pediatric populations, and efficacy of ACAM2000 in protecting non-human primates from lethal challenge with mpox virus. Before the eradication of smallpox disease, live vaccinia virus smallpox vaccines were administered routinely in all pediatric age groups, including neonates and infants, and were effective in preventing smallpox disease. During that time, live vaccinia virus was occasionally associated with serious complications in children, the highest risk being in infants younger than 12 months of age.

8.5 Geriatric Use

Clinical studies of ACAM2000 did not include sufficient numbers of subjects aged 65 and over to determine whether they respond differently from younger subjects. There are no published data to support the use of this vaccine in geriatric (persons >65 years) populations.

11 DESCRIPTION

ACAM2000 (Smallpox and Mpox (Vaccinia) Vaccine, Live), for scarification suspension for percutaneous use, is a live vaccinia virus vaccine. The virus is derived from plaque purification cloning from Dryvax (Wyeth Laboratories, Marietta, PA, calf lymph vaccine, New York City Board of Health Strain). The vaccine virus is grown in African Green Monkey kidney (Vero) cells and tested to be free of adventitious agents.

ACAM2000 is provided as a Lyophilized Antigen Component, Live of purified live virus containing the following excipients: 6-8 mM HEPES (pH 6.5-7.5), 2% human serum albumin USP, 0.5 – 0.7% sodium chloride USP, 5% mannitol USP, and trace amounts of neomycin and polymyxin B.

The Diluent Component for ACAM2000 contains 50% (v/v) Glycerin USP, 0.25% (v/v) Phenol USP in Water for Injection USP, supplied in clear glass vials containing 0.6 mL of diluent.

After reconstitution, each vial of ACAM2000 contains approximately 100 doses. A single dose is approximately 0.0025 mL.

The concentration of vaccinia virus is 1.0 - 5.0 x 10^8 plaque-forming units (PFU)/mL or 2.5-12.5 x 10^5 PFU/dose determined by plaque assay in Vero cells. ACAM2000 is administered by the percutaneous route (scarification) using 15 jabs of a stainless steel bifurcated needle that has been dipped into the vaccine.

12 CLINICAL PHARMACOLOGY

12.1 Mechanism of Action

Vaccinia virus is a member of the same taxonomic group (the Orthopoxvirus genus) as variola (which causes smallpox) and mpox viruses. Immunity induced by vaccinia virus cross-protects against variola and mpox viruses. Vaccinia virus causes a localized virus infection of the epidermis at the site of inoculation, surrounding dermal and subcutaneous tissues, and draining lymph nodes. Virus may be transiently present in blood and infects reticuloendothelial and other tissues. Langerhans cells in the epidermis are specific targets for the early stage of virus replication. The formation of a pustule (‘pock’ or ‘take’) at the site of inoculation provides evidence of protective immunity. The virus replicates within cells and viral antigens are presented to the immune system. Neutralizing antibodies and B and T cells provide long-term memory. The level of neutralizing antibody that protects against smallpox or mpox is unknown but >95% of persons undergoing primary vaccination develop neutralizing or hemagglutination inhibiting antibodies to vaccinia.

12.2 Pharmacodynamics

Cutaneous Response

The cutaneous responses following ACAM2000 vaccination are dependent on the immune status of the individual, potency of the vaccine, and vaccination technique. Two types of responses have been defined by the WHO Expert Committee on Smallpox and described by the CDC - Advisory Committee on Immunization Practices (ACIP). The responses include: a) major cutaneous reaction, which indicates that virus replication has taken place and vaccination was successful; or b) equivocal reaction. Equivocal reactions may be a consequence of pre-existing immunity adequate to suppress viral multiplication, vaccination technique failure, or use of inactive vaccine or vaccine that has lost potency.

Successful vaccination in persons who are vaccinia vaccine-naïve, termed primary vaccination, is represented by a major cutaneous reaction, defined as a vesicular or pustular lesion or an area of definite palpable induration or congestion surrounding a central lesion that might be a crust or an ulcer.

Persons who have been previously vaccinated (vaccinia-experienced) and are revaccinated may manifest a reduced cutaneous response compared to vaccinia vaccine naïve persons, but still exhibit an immune response to the vaccine. [see Dosage and Administration (2.7)].

Neutralizing Antibody and Cellular Immune Responses

Neutralizing antibodies are known to mediate protection against smallpox. The level of neutralizing antibody that is required to protect against smallpox and mpox has not been clearly established. Some studies indicate that persons with antibody titers > 1:32 are protected against smallpox. Neutralizing antibodies against vaccinia develop in >95% of individuals following primary vaccination, rise rapidly (by day 15-20 after vaccination) and may be boosted on revaccination. Antibody titers are highly variable. Titers may remain high for longer periods following two or more vaccinations than after a primary vaccination. The level of the neutralizing antibody response following primary vaccination is generally in proportion to the intensity of the cutaneous reaction. Cellular immune responses are also elicited by vaccination and may contribute to protection and immunological memory.

Virus Shedding

Virus is shed from the vaccination site during the period starting with the development of a papule (day 2-5); shedding ceases when the scab separates and the lesion is re-epithelialized, typically 3-6 weeks after vaccination. Steps should be taken in clinical use to reduce the risk of accidental infection of other sites in the vaccinated patient or of contact spread to other individuals [see Dosage and Administration (2.6) and Warnings and Precautions (5.10)].

13 NONCLINICAL TOXICOLOGY

13.1 Carcinogenesis, Mutagenesis, Impairment of Fertility

ACAM2000 has not been evaluated for carcinogenic or mutagenic potential, or for impairment of male or female fertility in animals.

13.2 Animal Toxicology and/or Pharmacology

The efficacy of ACAM2000 to protect Cynomolgus macaques (Macaca fascicularis) against mpox virus challenge was evaluated. Animals were administered placebo (ACAM2000 Diluent Component), ACAM2000 or Dryvax percutaneously (approximately 0.0025 mL each via scarification) on Day 0. On Day 61, all animals were challenged with an intravenous injection of mpox virus (3.8x10^7 PFU). 100% of animals vaccinated with ACAM2000 or Dryvax survived compared to 0% of animals that received placebo.

14 CLINICAL STUDIES

The effectiveness of ACAM2000 for the prevention of mpox is based on its effectiveness for the prevention of smallpox and efficacy in animal challenge studies [see Nonclinical Toxicology (13.2)].

The effectiveness of ACAM2000 for the prevention of smallpox was assessed by comparing the immunologic response of ACAM2000 to a previously U.S.-licensed live vaccinia virus smallpox vaccine, Dryvax, in two randomized, multi-center active-controlled clinical trials; one study in subjects who previously had not been vaccinated with smallpox vaccine (i.e., vaccinia-naïve subjects) and one study in subjects who had been vaccinated with smallpox vaccine >10 years previously (i.e., vaccinia-experienced subjects). In both trials, the co-primary efficacy endpoints were the proportion of subjects with a successful vaccination/revaccination and the geometric mean neutralizing antibody titer (GMT) on Day 30. Successful primary vaccination was defined as a major cutaneous reaction on Day 7 or 10 (Days 6 to 11, with allowable visit window). Successful revaccination was defined as development of any cutaneous lesion on Day 7 (± 1 day) of a measurable size. Successful revaccination was determined by a panel of experts who reviewed digital photographs of the cutaneous lesions.

The statistical method used to compare the proportion of subjects who were successfully vaccinated in the two vaccine groups was a test of noninferiority of ACAM2000 to Dryvax intended to rule out a greater than 5% margin of superiority of Dryvax for successful primary vaccination (Study 1) and a 10% margin of superiority of the comparator for successful revaccination (Study 2). Noninferiority was to be declared if the lower bound of the 1-sided 97.5% confidence interval (CI) for the percent difference between ACAM2000 and Dryvax exceeded -5% in vaccinia-naïve subjects and 10% in vaccinia-experienced subjects.

Analysis of the GMT was performed using a test of noninferiority of neutralizing antibody titer between ACAM2000 and Dryvax, intended to ensure that the ratio of the GMTs of ACAM2000: Dryvax was at least 0.5 (equivalent to the difference of the log10 (GMT) being at least -0.301).

In Study 1, a total of 1037 male and female vaccinia-naïve subjects, aged 18 to 30 years inclusive, primarily Caucasian (76%) were randomized in a 3:1 ratio to receive ACAM2000 (780 subjects) or comparator Dryvax (257 subjects). The ACAM2000 vaccinated subjects were further stratified to receive one of three lots (Lots A, B and C) at a 1:1:1 ratio (258, 264, and 258 subjects, respectively). All subjects were to be evaluated for their cutaneous response and a random subset was selected for evaluation of neutralizing antibody response.

In Study 2, a total of 1647 male and female vaccinia-experienced subjects, aged 31 to 84 years inclusive, primarily Caucasian (81%) were randomized in a 3:1 ratio to receive ACAM2000 (1242 subjects) or Dryvax (405 subjects). The ACAM2000 vaccinated subjects were further stratified to receive one of three lots (Lots A, B and C) at a 1:1:1 ratio (411, 417, and 414 subjects, respectively). All subjects were evaluated for their cutaneous response and a random subset was to be selected for evaluation of neutralizing antibody response.

Table 5 and Table 6 present the results of the primary efficacy analyses for both studies.

Table 5 Cutaneous Response (Vaccination Success) in Subjects Given ACAM2000 vs. Dryvax Vaccine, Studies 1 (vaccinia-naïve) and 2 (vaccinia-experienced)
Clinical Study | Study 1 ACAM2000 | Study 1 Dryvax | Study 2 ACAM2000 | Study 2 Dryvax
Size of Efficacy Evaluable (EE) Population(a) | 776 | 257 | 1189 | 388
Number of Vaccination Successes (%) | 747 (96) | 255 (99) | 998 (84) | 381 (98)
97.5% 1-sided CI by normal approx. on percent difference between ACAM2000 and Dryvax | -4.67% (b) | -- | -17% (c) | --
Non-Inferiority to Dryvax | Yes | -- | No | --
a Subjects who received study vaccine and were evaluated for a local cutaneous reaction within the protocol designated timeframe (assessment of local cutaneous reaction between Days 6 and 11 in Study 1 and Days 6 to 8 in Study 2) were included in the efficacy evaluable (EE) population.
b Since the critical value for the evaluation was declared to be -5%, ACAM2000 is considered to be non-inferior to Dryvax for this parameter.
c Since the critical value for the evaluation was declared to be -10%, ACAM2000 is not considered to be non-inferior to Dryvax for this parameter.

Table 6 Neutralizing Antibody Response in Subjects Given ACAM2000 vs. Dryvax Vaccine, Studies 1 (vaccinia-naïve) and 2 (vaccinia-experienced)
Clinical Study | Study 1 ACAM2000 | Study 1 Dryvax | Study 2 ACAM2000 | Study 2 Dryvax
Size of Antibody Evaluable Population(a) | 565 | 190 | 734 | 376
GMT(b) | 166 | 255 | 286 | 445
Log10 mean | 2.2 | 2.4 | 2.5 | 2.6
97.5% 1-sided CI by ANOVA on difference between ACAM2000 and Dryvax | -0.307(c) | -- | -0.275(d) | --
Meets Non-Inferiority to Dryvax | No | -- | Yes | --
a A randomly selected sample of subjects who received study vaccine and had samples collected for neutralizing antibody response at Baseline and at the designated timepoint post vaccination were included in the antibody evaluable (AnE) population.
b GMT – Geometric mean neutralizing antibody titer as measured by Vaccinia 50% plaque reduction neutralization test.
c Since the critical value for the evaluation was declared to be -0.301, ACAM2000 is not considered to be non-inferior to Dryvax for this parameter.
d Since the critical value for the evaluation was declared to be -0.301, ACAM2000 is considered to be non-inferior to Dryvax for this parameter

The primary determinant for an effective immune response in those naïve to vaccine is a major cutaneous reaction. An efficacy evaluable (EE) population was used for determination of vaccination success. ACAM2000 was non-inferior to Dryvax in the EE population when eliciting a major cutaneous reaction. The measure of the strength of the generated antibody response in vaccinia-naïve subjects was similar between vaccine groups but did not meet the predefined criterion for non-inferiority. Among subjects who were vaccinia-experienced, development of a major cutaneous response after revaccination with vaccinia-based vaccines may not provide an accurate measure of the strength of the immune response because the preexisting immunity modifies the scope of the cutaneous response. In vaccinia-experienced subjects, ACAM2000 did not meet the non-inferiority criterion for cutaneous response but was non-inferior to Dryvax with regard to the strength of the neutralizing antibody immune response. Therefore, ACAM2000 was non-inferior to Dryvax in the rate of major cutaneous reaction in those naïve to the vaccine only, and non-inferior to Dryvax in the strength of the neutralizing antibody immune response in those previously exposed to vaccinia-based vaccines.

15 REFERENCES

1. “Comparison of Reactions for First-Time Vaccinees and Revaccinees,” Centers for Disease Control and Prevention, 5 December 2016. [Online]. Materials developed by United States Center for Disease Control and Prevention (CDC). Reference to specific commercial products, manufacturers, companies, or trademarks does not constitute its endorsement or recommendation by the U.S. Government, Department of Health and Human Services, or Centers for Disease Control and Prevention. The material is otherwise available on the agency website for no charge. Available: https://www.cdc.gov/smallpox/clinicians/comparison-vaccinees-images.html [Accessed 24 November 2022].
2. Petersen BW, Harms TJ, Reynolds MG, Harrison LH. Use of Vaccinia Virus Smallpox Vaccine in Laboratory and Health Care Personnel at Risk for Occupational Exposure to Orthopoxviruses – Recommendations of the Advisory Committee on Immunization Practices (ACIP), 2015. MMWR Morb Mortal Wkly Rep. 2016; 65(10):257-262.
3. Lane J, Millar J. Risks of smallpox vaccination complications in the United States. Am J Epidemiol. 1971;93:238-240.
4. Lane, JM, Ruben FL, Neff JM, Millar JD. Complications of smallpox vaccination, 1968: results of ten statewide surveys. J Infect Dis. 1970;122(4):303-309.
5. Poland GA, Grabenstein JD, Neff JM. The US smallpox vaccination program: a review of a large modern era smallpox vaccination implementation program. Vaccine. 2005 Mar 18;23(17-18):2078-81. doi: 10.1016/j.vaccine.2005.01.012. PMID: 15755574.

16 HOW SUPPLIED / STORAGE AND HANDLING

16.1 How Supplied

ACAM2000 is supplied as 2 components as follows:

- Lyophilized Antigen Component, Live (labels state: Smallpox (Vaccinia) Vaccine, Live
  ACAM2000®)
  - Vial (NDC 71665-430-01 and NDC 71665-330-01)
  - Each carton (NDC 71665-430-02 and NDC 71665-330-02) contains 50 multiple-dose clear glass vials
  - Each case (NDC 71665-430-03 and NDC 71665-330-03) contains 8 cartons
- Diluent Component (labels may state: Diluent for Smallpox (Vaccinia) Vaccine, Live,
  ACAM2000®)
  - Vial (NDC 71665-440-01 and NDC 71665-340-01)
  - Each carton (NDC 71665-440-02 and NDC 71665-340-02) contains 50 clear glass vials
  - Each case (NDC 71665-440-03 and NDC 71665-340-03) contains 8 cartons

Bifurcated needles are supplied separately. Tuberculin syringes and needles (1 mL, 25-gauge x 5/8” needles) for vaccine reconstitution are supplied separately.

The stoppers of the vials containing the Lyophilized Antigen Component, Live and the stoppers of the vials containing the Diluent Component are not made with natural rubber latex.

16.2 Storage and Handling

The Lyophilized Antigen Component, Live is supplied in cartons and vials labeled “Smallpox (Vaccinia) Vaccine, Live, ACAM2000.” The Diluent Component may be supplied in cartons and vials labeled “Diluent for Smallpox (Vaccinia) Vaccine, Live, ACAM2000.” Storage and Handling conditions are described below.

Lyophilized Antigen Component, Live

Lyophilized Antigen Component, Live is shipped frozen. During shipment, the Lyophilized Antigen Component, Live should be maintained at a temperature of -10°C (14°F) or colder.

Store in a freezer with an average temperature of -25°C to -15°C (-13°F to 5°F).

The Lyophilized Antigen Component, Live may be stored at refrigerated temperatures of 2°C to 8°C (36°F to 46°F) for up to 18 months or until expiry whichever comes first. Calculate and record the 18-month expiry date when Lyophilized Antigen Component, Live is moved from freezer to refrigerator.

Diluent Component

The Diluent Component is supplied in separate cartons and is shipped at 2°C to 30°C (36°F to 86°F).

Store at 15°C to 30°C (59°F to 86°F).

Reconstituted ACAM2000

After reconstitution, store in a refrigerator at 2°C to 8°C (36°F to 46°F) for up to 30 days. ACAM2000 may be kept at 20°C to 25°C (68°F to 77°F) for up to 8 hours. Discard unused reconstituted ACAM2000 as a biohazardous material [see Dosage and Administration (2.5)].

ACAM2000 contains live vaccinia virus that is transmissible and should be handled as an infectious agent once vials are open [see Dosage and Administration (2.3 and 2.5)].

17 PATIENT COUNSELING INFORMATION

Instruct the vaccine recipient or caregiver to read the FDA-approved Medication Guide for ACAM2000. Provide pregnancy registry information to individuals vaccinated with ACAM2000 who are or may become pregnant [see Use in Specific Populations (8.1)].

Serious Complications of Vaccination

Vaccine recipients or caregivers must be informed of the major serious adverse reactions associated with vaccination, including myocarditis and/or pericarditis, progressive vaccinia in immunocompromised persons, eczema vaccinatum in persons with skin disorders, auto- and accidental inoculation, generalized vaccinia, urticaria, erythema multiforme major (including Stevens-Johnson syndrome) and fetal vaccinia in pregnant women.

Protecting Contacts at Highest Risk for Adverse Events

Vaccine recipients or caregivers must be informed that they should avoid contact with individuals at high risk of serious adverse effects of vaccinia virus, for instance, those with past or present eczema, immunodeficiency states including HIV infection, pregnancy, or infants less than 12 months of age.

Self-inoculation and Spread to Close Contacts

Vaccine recipients or caregivers must be advised that virus is shed from the cutaneous lesion at the site of inoculation from approximately Day 2 post-vaccination until the scab separates and the lesion is re-epithelialized typically 3 to 6 weeks after primary vaccination. Vaccinia virus may be transmitted by direct physical contact. Accidental infection of skin at sites other than the site of intentional vaccination (self-inoculation) may occur by trauma or scratching. Contact spread may also result in accidental inoculation of household members or other close contacts (including sexual contacts). The result of accidental infection is a pock lesion(s) at an unwanted site(s) in the vaccinee or contact and resembles the vaccination site. Self-inoculation occurs most often on the face, eyelid, nose, anus and mouth, but lesions at any site of traumatic inoculation can occur. Self-inoculation of the eye may result in ocular vaccinia, a potentially serious complication.

Care of the Vaccination Site and Potentially Contaminated Materials

Vaccine recipients or caregivers must be given the following instructions:

- The vaccination site must be completely covered with gauze secured loosely with first aid adhesive tape. If the vaccine recipient is directly involved in patient care, the gauze may be covered with a semipermeable dressing that allows passage of air but not fluids. Keep the site covered until the scab falls off on its own.
- The vaccination site must be kept dry. Normal bathing may continue, but cover the vaccination site with waterproof bandage when bathing. Do not scrub the site. Cover the vaccination site with loose gauze held in place with first aid adhesive tape after bathing.
- Don’t scratch the vaccination site. Don’t scratch or pick at the scab.
- Do not touch the lesion or soiled gauze, semipermeable dressing, or bandages and then touch other parts of the body such as the eyes, anal and genital areas where the virus can spread.
- After changing the gauze, semipermeable dressing, or bandages, or touching the site, wash hands thoroughly with soap and water or >60% alcohol-based hand-rub solutions.
- To prevent transmission to contacts, physical contact of objects that have come into contact with the lesion (e.g., soiled bandages, clothing, fingers) must be avoided.
- Wash separately clothing, towels, bedding or other items that may have come in direct contact with the vaccination site or drainage from the site, with using hot water with detergent and/or bleach. Wash hands afterwards.
- Soiled and contaminated gauze, semipermeable dressings, and bandages must be placed in plastic bags for disposal.
- The vaccinee must wear a shirt with sleeves that covers the vaccination site as an extra precaution to prevent spread of the vaccinia virus. This is especially important in case of close physical contact with others.
- The vaccinee must change the gauze and semipermeable dressing every 1 to 3 days. This will keep skin at the vaccination site intact and minimize softening.
- Do not put salves or ointments on the vaccination site.
- When the scab falls off, throw it away in a sealed plastic bag and wash hands afterwards.

Manufactured by

Emergent Product Development Gaithersburg Inc.
Gaithersburg, MD USA 20879
License No. 2089

Any and all Emergent BioSolutions Inc. brand, product, service and feature names, logos and slogans are trademarks or registered trademarks of Emergent BioSolutions Inc. or its subsidiaries in the United States or other countries. All rights reserved.

MEDICATION GUIDE
ACAM2000®
Smallpox and Mpox (Vaccinia) Vaccine, Live
Please read this Medication Guide and talk to your healthcare provider before you receive ACAM2000.

What is the most important information I should know about ACAM2000?
ACAM2000 contains live vaccinia virus (a “pox”-type virus) that can be spread to individuals who have close contact with the vaccinated individual. ACAM2000 can cause serious complications in vaccinated individuals and in their close contacts to whom the vaccine virus has spread.
Serious complications of ACAM2000 include:

- Myocarditis (inflammation of the heart muscle) and pericarditis (inflammation of the lining outside the heart). Most cases have occurred within 1-2 weeks after vaccination. Symptoms of myocarditis and pericarditis include:
  - Chest pain
  - Shortness of breath or difficulty breathing
  - Feelings of having a fast-beating, fluttering, or pounding heart
Symptoms of myocarditis and pericarditis may be different in children and may also include:
  1. Fainting
  2. Unusual and persistent irritability
  3. Unusual and persistent poor feeding
  4. Unusual and persistent fatigue or lack of energy
  5. Persistent vomiting
  6. Persistent pain in the abdomen
  7. Unusual and persistent cool, pale skin
- Inflammation of the brain or spinal cord
- Serious skin infections such as a rash caused by widespread infection of the skin (known as eczema vaccinatum), buildup of inflamed tissue around the vaccination site that may at first look like a bullseye and will grow into a large, non-healing sore (known as progressive vaccinia).
- Spreading of the vaccine virus through the blood to other parts of your body
- Fetal death
- Accidental infection of the eye (which may cause swelling of the cornea causing watery painful eyes and blurred vision, scarring of the cornea, and blindness)
- Severe allergic reaction after vaccination

The risks for serious vaccine side effects are greater for people who:

- have heart problems or a history of heart problems
- are taking steroid eye drops or ointment
- have a weakened immune system
- have skin problems such as eczema, atopic dermatitis, burns, impetigo, contact dermatitis, chickenpox, shingles, psoriasis, or uncontrolled acne
- are less than 1 year old
- are pregnant or become pregnant within 6 weeks after vaccination

Tell your healthcare provider if any of the above apply to you or anyone with whom you live, work or have close contact.
The risk for experiencing serious vaccination complications must be weighed against the risks for experiencing a potentially severe or fatal smallpox or mpox infection.

What is ACAM2000?
ACAM2000 is a vaccine used to prevent smallpox and mpox disease. It is for use in people of any age who have a high chance of getting smallpox or mpox disease.
If you are at a high risk for being exposed to smallpox and/or mpox, you should discuss with your healthcare provider whether you should receive ACAM2000.

Who should not get ACAM2000?
Individuals with severely weakened systems such as those undergoing bone marrow transplantation or individuals with weakened immune systems who require isolation should not get ACAM2000.
If you are unable to receive ACAM2000 because of a problem with your immune system, talk to your healthcare provider about other options to protect against smallpox and mpox.

What are the ingredients in ACAM2000?
ACAM2000 contains the following ingredients: live vaccinia virus grown in African Green Monkey kidney (Vero) cells, HEPES buffer, human serum albumin, sodium chloride, mannitol, trace amounts of the antibiotics neomycin and polymyxin B, Glycerin, and Phenol.

How is ACAM2000 given?

ACAM2000 is given “percutaneously.” Your healthcare provider will make 15 pokes in the skin of your upper arm with a two-prong needle holding a small drop of ACAM2000. The pokes are not deep but will cause a drop of blood to form. Where the 15 pokes are made is called the vaccination site.

What should I avoid after getting vaccinated with ACAM2000?
For 6 weeks after vaccination and until the vaccination site has healed, avoid:

- Getting pregnant or getting your partner pregnant.
- Spreading the vaccine virus to unvaccinated individuals, especially infants (including while breastfeeding), pregnant individuals, and individuals with a weakened immune system. The virus can be spread by physical contact (including sexual contact) and by sharing a bed, clothes, towels, linen, or toiletries with unvaccinated people.
- Donating blood or organs.
- Rubbing, scratching, or touching the vaccination site.

How do I care for the ACAM2000 vaccination site?
Your vaccination site is considered “infectious” from the time you get vaccinated until a scab forms and falls off and the skin at the vaccination site is fully healed. It is important to care for the vaccination site properly so that the virus doesn’t spread to other parts of your body or to other people.
It is important to ALWAYS:

- Wear gauze secured loosely with first aid adhesive tape to cover the entire vaccination site.
- Wear sleeves to cover the bandage.
- Cover the vaccination site with a semipermeable dressing on top of the gauze to provide additional protection against spread of the virus if you are a healthcare worker. The dressing should allow passage of air to the vaccination site, but not allow passage of fluid.
- Wash your hands with soap and warm water or alcohol-based cleansers after contact with the vaccination site, bandages or clothes, towels, or sheets that might be contaminated with the vaccine virus. Wear gloves when changing bandages or caring for your vaccination site.
- Change your gauze when it begins to soak through (at least every 1 to 3 days).
- Throw away gloves and used gauze, semipermeable dressings, and bandages in sealed plastic bags with a small amount of bleach to kill the virus.
- Cover the vaccination site with a waterproof bandage during bathing or showering. If the vaccination site gets wet, dry the site with toilet paper and flush it. Cover the vaccination site with a loose gauze bandage after bathing or showering to allow it to dry out.
- Use a waterproof bandage on the vaccination site while exercising if you exercise enough to cause sweat to drip.
- Wash clothing, towels, bedding or other items that may have come in contact with the vaccination site separately from other wash. Use hot water with detergent and bleach.
- Throw the scab away in a sealed plastic bag with a small amount of bleach when it falls off. Wash your hands afterwards.

Do NOT:

- Do not use creams or ointments on the vaccination site.
- Do not scratch or pick at the vaccination site.
- Do not touch or scrub vaccination site while taking a bath or shower.
- Do not use a bandage that blocks air from the vaccination site. This could cause the skin at the vaccination site to soften and wear away.

What should I expect at the vaccination site during the weeks following vaccination with ACAM2000?

If you have never been vaccinated with a smallpox or mpox vaccine, vaccination is successful if a red and itchy bump forms at the vaccination site in 2 to 5 days. Over the next few days, the bump becomes a blister and fills with pus. The blister then dries up and a scab forms. The scab falls off after 3 to 6 weeks, leaving a scar. The expected responses are shown below.

Expected response at ACAM2000 vaccination site in people never vaccinated with a smallpox or mpox vaccine

Note: After 6 to 11 days, check to be sure that your vaccination site looks like one of the pictures above. If it does not look like this, see your healthcare provider because you may need to be revaccinated.

If you have been previously vaccinated with a smallpox or mpox vaccine, you may have a reduced response to ACAM2000 compared to those not previously vaccinated. In most previously vaccinated individuals a red, itchy bump forms at the vaccination site in 6 to 8 days. The expected responses are shown below for individuals who were previously vaccinated with ACAM2000 or smallpox vaccines used historically.

Expected response at ACAM2000 vaccination site in people previously vaccinated with a smallpox or mpox vaccine

Note: If the expected response shown above does not occur you still may have been successfully vaccinated and you do not need another dose.

Pictures are from the United States Centers for Disease Control and Prevention (CDC). Reference to specific commercial products, manufacturers, companies, or trademarks does not constitute its endorsement or recommendation by the U.S. Government, Department of Health and Human Services, or Centers for Disease Control and Prevention. The material is otherwise available on the agency website for no charge. See also: https://www.cdc.gov/smallpox/clinicians/comparison-vaccinees-images.html

If you need medical care within 6 weeks after your vaccination, tell your healthcare provider that you were vaccinated with ACAM2000.

What are other possible side effects of ACAM2000?

- redness at the vaccination site
- pain at the vaccination site
- swelling at the vaccination site
- itching at the vaccination site
- swollen lymph nodes
- fever

- headache
- muscle ache
- rash
- fatigue
- feeling unwell

Tell your healthcare provider about any side effect that bothers you or that does not go away.
To report SUSPECTED SIDE EFFECTS (ADVERSE REACTIONS), contact Emergent BioSolutions at 1-877-246-8472 and medicalinformation@ebsi.com or VAERS at 800-822-7967 and https://vaers.hhs.gov

Does ACAM2000 interfere with any laboratory tests?
ACAM2000 may cause some tests for Tuberculosis (TB) or Syphilis to give the wrong result. If you need to be tested for TB or Syphilis within 6 weeks of receiving ACAM2000, tell your healthcare provider that you received ACAM2000.

General information about the safe and effective use of ACAM2000
This Medication Guide provides a summary of the most important information about ACAM2000. Medicines are sometimes prescribed for purposes other than those listed in the Medication Guide. If you would like more information or have any questions, talk to your healthcare provider. You can ask your healthcare provider for information about ACAM2000 that is written for healthcare professionals. The vaccine should not be used for a condition other than that for which it is prescribed.

Manufactured by:
Emergent Product Development Gaithersburg Inc. Gaithersburg, MD 20879
Any and all Emergent BioSolutions Inc. brand, product, and service are trademarks or registered trademarks of Emergent BioSolutions Inc. or its subsidiaries in the United States or other countries. All rights reserved.
This Medication Guide has been approved by the U.S. Food and Drug Administration.
Revised: 08/2024

LBL040018-02

Health Care Provider Letter

02/2025
IMPORTANT PRESCRIBING INFORMATION

Subject: ACAM2000® [Smallpox and Mpox (Vaccinia) Vaccine, Live] supplied in vials, cartons and cases with previously approved labels

Dear Health Care Provider:

The purpose of this letter is to notify you that you have received ACAM2000 supplied in vials, cartons, and cases with previously approved labels.

The previously approved labels do not include:

- The revised nonproprietary name for ACAM2000: Smallpox and Mpox (Vaccinia) Vaccine, Live
- The revised names for the two components of ACAM2000 (i.e., Lyophilized Antigen Component, Live and Diluent Component).

The previously approved labels include the previous nonproprietary name for ACAM2000: Smallpox (Vaccinia) Vaccine, Live and refer to the Diluent Component as “Diluent for Smallpox (Vaccinia) Vaccine, Live, ACAM2000®.”

The components of ACAM2000 have not changed despite the revised names. The revised names for the vaccine components are used in the US Prescribing Information (USPI) including in the Dosage and Administration and the How Supplied/Storage and Handling sections. Complete reconstitution instructions and storage and handling are described in the USPI.

You will continue to receive ACAM2000 components packaged with the previously approved vial, carton, and case labels until this supply is depleted or expired.

The ACAM2000 nonproprietary name was revised when the indication for ACAM2000 vaccine was expanded on August 29, 2024, to include the prevention of mpox disease in individuals determined to be at high risk for mpox infection. This required revisions to the USPI and Medication Guide to include the new nonproprietary name and indication. Updates were also made to the Dosage and Administration and How Supplied/Storage and Handling sections of the USPI. Changes were made to the product packaging labelling (vial, carton and case labels) to make them consistent with the USPI.

Indications and Usage

ACAM2000 is a vaccine indicated for active immunization for the prevention of smallpox and mpox disease in individuals determined to be at high risk for smallpox or mpox infection.

Reporting Adverse Events

Report adverse events following use of ACAM2000 to Emergent BioSolutions at 1-877-246-8472 and medicalinformation@ebsi.com or to VAERS at 800-822-7967 and https://vaers.hhs.gov.

You may contact our medical information department if you have any questions about the information contained in this letter or the safe and effective use of ACAM2000 at 1-877-246-8472 or medicalinformation@ebsi.com

This letter is not intended as a complete description of the benefits and risks related to the use of ACAM2000; please refer to the enclosed full prescribing information and Medication Guide.

Sincerely,

Company Representative

PACKAGE/LABEL PRINCIPAL DISPLAY PANEL – Antigen Vial Labels

Lyophylized Antigen Component, Live

NOT TO BE USED ALONE

Reconstitute with Diluent
Component to form ACAM2000®.
After reconstitution vial contains
100 nominal doses of approx..
0.0025 mL each.
For percutaneous use.
Lot No.
Frozen Exp. Date: DDMMMYYYY
Refrig. Exp. Date:

Vial 1 of 2

Store at -25°C to -15°C (-13°F to
5°F). Store at 2°C to 8°C (36°F to
46°F) for up to 18 months. After
reconstitution store at 2°C to 8°C
(36°F to 46°F) for up to 30 days.

Reconst. Date:

Manufactured by:
Emergent Product
Development Gaithersburg Inc.
Gaithersburg, MD 20879 USA, Lic. 2089

LBL040437-01

‘Rx only’

STRATEGIC NATIONAL STOCKPILE USE ONLY

Smallpox (Vaccinia) Vaccine,
Live ACAM2000®

'Rx Only'. For percutaneous
inoculation with Bifurcated Needle
only. Do not administer by injection.
Contains trace amounts of antibiotics.

Lot No.

Mfg. Date:

Recon Date:

Store at 2-8°C (36-46°F). Use within
30 days of reconstitution.

Fill volume: 0.3 mL/100 doses.

Approximate Dose: 2.5µ L

Potency: 1-5x10^8 PFU/mL

Manufactured by:
Emergent Product
Development Gaithersburg Inc.
Gaithersburg, MD 20879 USA, Lic. 2089

COMPONENT # LBL040020-01

PACKAGE/LABEL PRINCIPAL DISPLAY PANEL – Antigen Carton Labels

Lyophylized Antigen Component, Live

Vial 1 of 2

NOT TO BE USED ALONE

Reconstitute with Diluent Component to form Smallpox and Mpox (Vaccinia) Vaccine,
Live (ACAM2000®)

For percutaneous use. A single dose is approximately 0.0025 mL.

Contains trace amounts of antibiotics (Neomycin and Polmyxin B).

For additional information see ACAM2000 Prescribing Information. A Medication Guide for
ACAM2000 is available in electronic format and is to be provided to each potential vaccinee.

Store at -25°C to -15°C (-13°F to 5°F).
May be stored at 2°C to 8°C (36°F to 46°F) for up to 18 months.
After reconstitution, store at 2°C to 8°C (36°F to 46°F) and use within 30 days.

Frozen Expiration Date: DDMMMYYYY Lot No. XXXXXXX
Refrig. Exp. Date:

Contents: 50 vials; After reconstitution with Diluent Component each vial contains 100
nominal doses.

Manufactured by:
Emergent Product Development Gaithersburg Inc.
Gaithersburg, MD 20879 USA, Lic. 2089

LBL040022-02

‘Rx only’

EMERGENT®

STRATEGIC NATIONAL STOCKPILE USE ONLY

Smallpox (Vaccinia) Vaccine, Live
ACAM2000®

'Rx Only'. For percutaneous inoculation with Bifurcated Needle only. Do not administer
by injection. Live Vaccinia virus derived from cloning Dryvax® (Wyeth Laboratories,
NYCBH Strain) and grown in Vero cells. For full prescribing and product information, see
ACAM2000® Package Insert.
Contains trace amounts of antibiotics (Neomycin and Polymyxin B).
A Medication Guide for ACAM2000® is available in electronic format, and is to be
provided to each potential vaccinee.

Approximate dose: 2.5 µL
Lot No. XXXXXXX

Potency: 1-5x10^8 PFU/mL
Expiration Date: DDMMMYYYY

Store at -25 to -15°C (-13 to 5°F) until distributed for use. Upon distribution, product
may be stored at 2-8°C (36-46°F) for up to 18 months. Do not use after expiration date.
Store reconstituted vaccine at 2-8°C (36-46°F). Use within 30 days of reconstitution date.

Manufactured by:
Emergent Product Development Gaithersburg Inc.
Gaithersburg, MD 20879 USA, Lic. 2089

Contents: 50 Vials; 0.3 mL/100 doses/vial

Component # LBL040022-01

emergent
biosolutions®

Lyophylized Antigen Component, Live

Vial 1 of 2

NOT TO BE USED ALONE

Reconstitute with Diluent Component to form Smallpox and Mpox (Vaccinia) Vaccine,
Live (ACAM2000®)

For percutaneous use. A single dose is approximately 0.0025 mL.

Contains trace amounts of antibiotics (Neomycin and Polmyxin B).

For additional information see ACAM2000 Prescribing Information. A Medication Guide for
ACAM2000 is available in electronic format and is to be provided to each potential vaccinee.

Store at -25°C to -15°C (-13°F to 5°F).
May be stored at 2°C to 8°C (36°F to 46°F) for up to 18 months.
After reconstitution, store at 2°C to 8°C (36°F to 46°F) and use within 30 days.

Frozen Expiration Date: DDMMMYYYY Lot No. XXXXXXX
Refrig. Exp. Date:

Contents: 50 vials; After reconstitution with Diluent Component each vial contains 100
nominal doses.

Manufactured by:
Emergent Product Development Gaithersburg Inc.
Gaithersburg, MD 20879 USA, Lic. 2089

LBL040023-02

‘Rx only’

EMERGENT®

STRATEGIC NATIONAL STOCKPILE USE ONLY

Smallpox (Vaccinia) Vaccine, Live
ACAM2000®

'Rx Only'. For percutaneous inoculation with Bifurcated Needle only. Do not administer
by injection. Live Vaccinia virus derived from cloning Dryvax® (Wyeth Laboratories,
NYCBH Strain) and grown in Vero cells. For full prescribing and product information, see
ACAM2000® Package Insert.
Contains trace amounts of antibiotics (Neomycin and Polymyxin B).
A Medication Guide for ACAM2000® is available in electronic format, and is to be
provided to each potential vaccinee.

Approximate dose: 2.5 µL
Lot No. XXXXXXX

Potency: 1-5x10^8 PFU/mL
Expiration Date: DDMMMYYYY

Store at -25 to -15°C (-13 to 5°F) until distributed for use. Upon distribution, product
may be stored at 2-8°C (36-46°F) for up to 18 months. Do not use after expiration date.
Store reconstituted vaccine at 2-8°C (36-46°F). Use within 30 days of reconstitution date.

Manufactured by:
Emergent Product Development Gaithersburg Inc.
Gaithersburg, MD 20879 USA, Lic. 2089

Contents: 50 Vials; 0.3 mL/100 doses/vial

Component # LBL040023-01

emergent
biosolutions®

PACKAGE/LABEL PRINCIPAL DISPLAY PANEL – Antigen Case Labels

Lyophylized Antigen Component, Live

Vial 1 of 2

NOT TO BE USED ALONE

Reconstitute with Diluent Component to form Smallpox and Mpox (Vaccinia) Vaccine,
Live (ACAM2000®)

For percutaneous use. A single dose is approximately 0.0025 mL.

Contains trace amounts of antibiotics (Neomycin and Polmyxin B).

For additional information see ACAM2000 Prescribing Information. A Medication Guide for
ACAM2000 is available in electronic format and is to be provided to each potential vaccinee.

Store at -25°C to -15°C (-13°F to 5°F).
May be stored at 2°C to 8°C (36°F to 46°F) for up to 18 months.
After reconstitution, store at 2°C to 8°C (36°F to 46°F) and use within 30 days.

Frozen Expiration Date: DDMMMYYYY Lot No. XXXXXXX
Refrig. Exp. Date:

Contents: 8 Cartons of 50 vials; After reconstitution with Diluent Component each vial contains
100 nominal doses.

Manufactured by:
Emergent Product Development Gaithersburg Inc.
Gaithersburg, MD 20879 USA, Lic. 2089

LBL040021-02

‘Rx only’

EMERGENT®

STRATEGIC NATIONAL STOCKPILE USE ONLY

Smallpox (Vaccinia) Vaccine, Live
ACAM2000®

'Rx Only'. For percutaneous inoculation with Bifurcated Needle only. Do not administer by injection.
Live Vaccinia virus derived from cloning Dryvax® (Wyeth Laboratories, NYCBH Strain) and grown in
Vero cells. For full prescribing and product information, see ACAM2000® Package Insert.
Contains trace amounts of antibiotics (Neomycin and Polymyxin B).
A Medication Guide for ACAM2000® is available in electronic format, and is to be
provided to each potential vaccinee.

Approximate dose: 2.5 µL
Lot No. XXXXXXX

Potency: 1-5x10^8 PFU/mL
Expiration Date: DDMMMYYYY

Store at -25 to -15°C (-13 to 5°F) until distributed for use. Upon distribution, product may
be stored at 2-8°C (36-46°F) for up to 18 months. Do not use after expiration date. Store
reconstituted vaccine at 2-8°C (36-46°F). Use within 30 days of reconstitution date.

Manufactured by:
Emergent Product Development Gaithersburg Inc.
Gaithersburg, MD 20879 USA, Lic. 2089

Contents: 8 Boxes of 50 Vials; 0.3 mL/100 doses/vial

Component # LBL040021-01

emergent
biosolutions®

PACKAGE/LABEL PRINCIPAL DISPLAY PANEL – Diluent Vial Labels

Diluent Component

NOT TO BE USED ALONE

Add 0.3 mL to one of
Lyophilized Antigen
Component, Live to form
ACAM2000®

Lot No. / Exp. Date:

Vial 2 of 2

Store at 15°C to 30°C
(59°F to 86°F)

50% (v/v) Glycerin USP
0.25% (v/v) Phenol USP

Manufactured by:
Emergent Product Development
Gaithersburg Inc.
Gaithersburg MD 20879 USA

LBL040438-01

Diluent for Smallpox
(Vaccinia) Vaccine, Live,
ACAM2000®

50% (v/v) Glycerin USP
0.25% (v/v) Phenol USP
in Water for Injection USP

Lot No. / Exp. Date:

Store at 15-30°C (59-86°F)

For vaccine reconstitution –
do not administer by injection

Fill Volume: 0.6mL – Transfer
0.3mL to vaccine vial

Manufactured by:
Emergent Product Development
Gaithersburg Inc.
Gaithersburg MD 20879 USA

50000001 151-H02

PACKAGE/LABEL PRINCIPAL DISPLAY PANEL – Diluent Carton Labels

Diluent Component

NOT TO BE USED ALONE

Vial 2 of 2

Use to reconstitute Lyophilized Antigen Component, Live to form Smallpox
and Mpox (Vaccinia) Vaccine, Live (ACAM2000®)

50% (v/v) Glycerin USP, 0.25% (v/v) Phenol USP, in Water for Injection USP

Lot No.
Expiration Date:

Store at 15°C to 30°C (59°F to 86°F)
Contents: 50 Vials of Diluent Component

Manufactured by:
Emergent Product Development Gaithersburg Inc.
Gaithersburg, MD 20879 USA

LBL040025-02

EMERGENT®

Diluent for Smallpox (Vaccinia) Vaccine, Live,
ACAM2000®

50% (v/v) Glycerin USP, 0.25% (v/v) Phenol USP, in Water for Injection USP
For vaccine reconstitution. Do not administer by injection.

Lot No.
Expiration Date:

Store at 15-30°C (59-86°F)

Manufactured by:
Emergent Product Development Gaithersburg Inc.
Gaithersburg, MD 20879 USA

Contents: 50 Vials

876389-H02

emergent
biosolutions®

PACKAGE/LABEL PRINCIPAL DISPLAY PANEL – Diluent Case Labels

Diluent Component

NOT TO BE USED ALONE

Vial 2 of 2

Use to reconstitute Lyophilized Antigen Component, Live to form Smallpox and
Mpox (Vaccinia) Vaccine, Live (ACAM2000®)

50% (v/v) Glycerin USP, 0.25% (v/v) Phenol USP, in Water for Injection USP

Lot No.
Expiration Date:

Store at 15°C to 30°C (59°F to 86°F)
Contents: 8 Cartons of 50 Vials of Diluent Component

Manufactured by:
Emergent Product Development Gaithersburg Inc.
Gaithersburg, MD 20879 USA

LBL040026-02

EMERGENT

Diluent for Smallpox (Vaccinia) Vaccine, Live,
ACAM2000®

50% (v/v) Glycerin USP, 0.25% (v/v) Phenol USP, in Water for Injection USP
For vaccine reconstitution. Do not administer by injection.

Lot No.
Expiration Date:

Store at 15-30°C (59-86°F)
Manufactured by:
Emergent Product Development Gaithersburg Inc.
Gaithersburg, MD 20879 USA

Contents: 8 Boxes of 50 Vials

876390-H02

emergent
biosolutions®